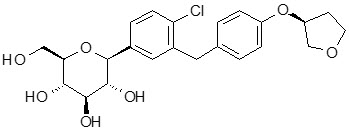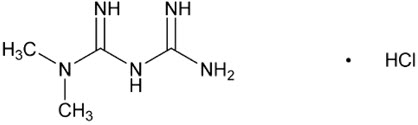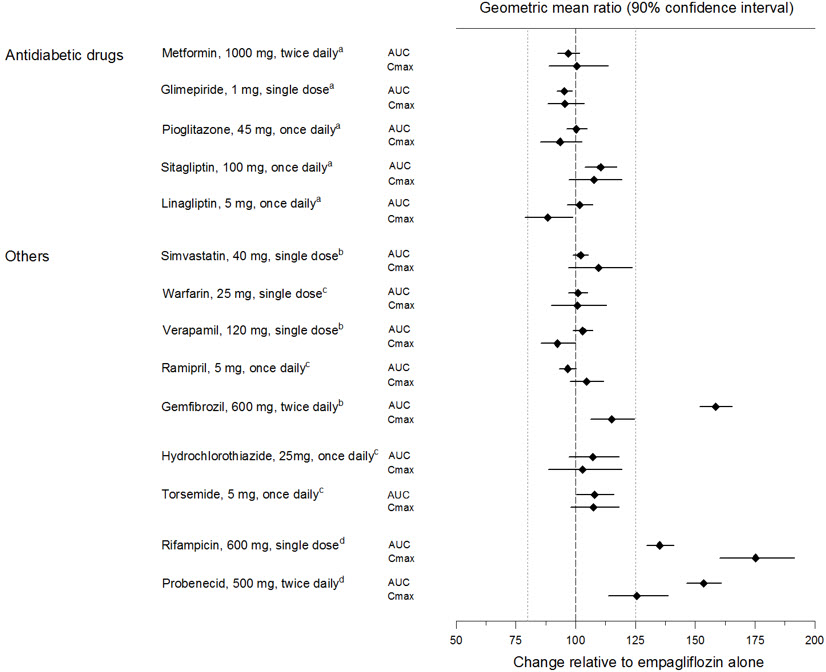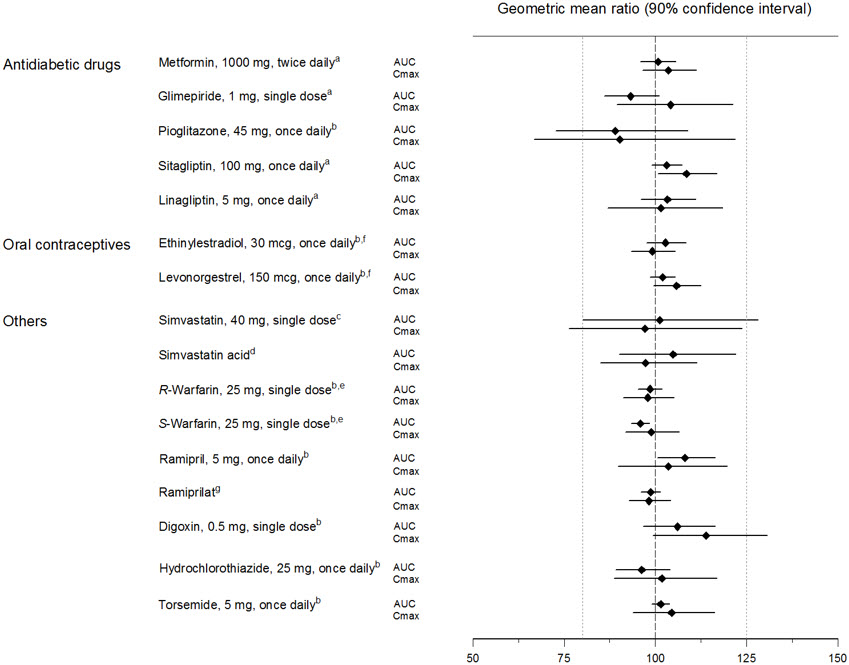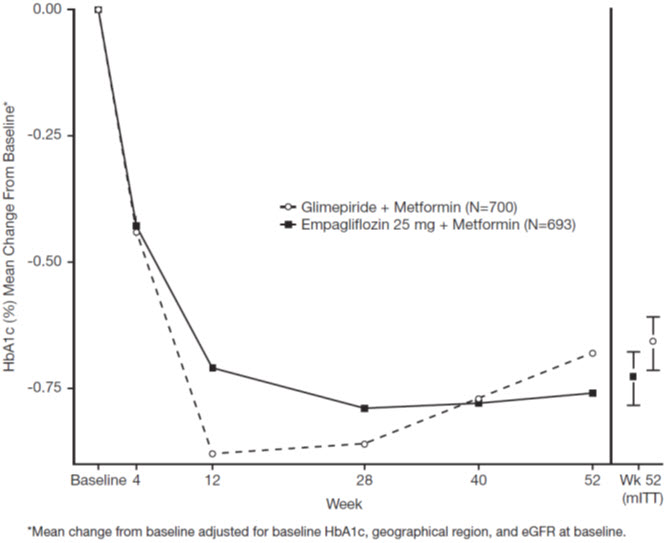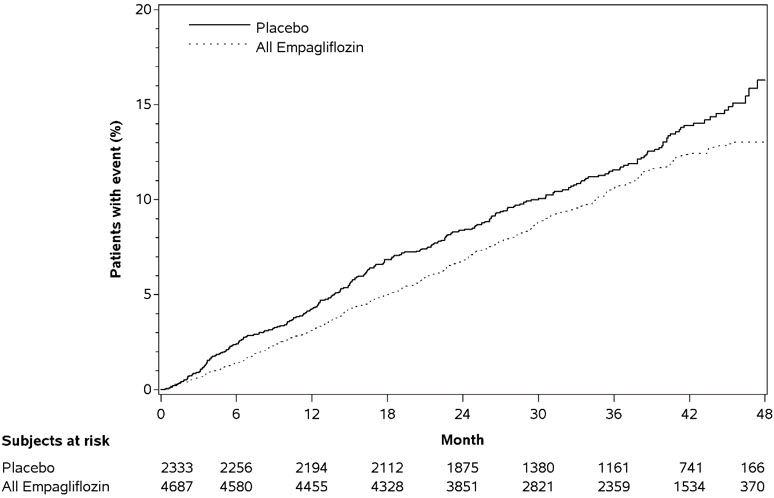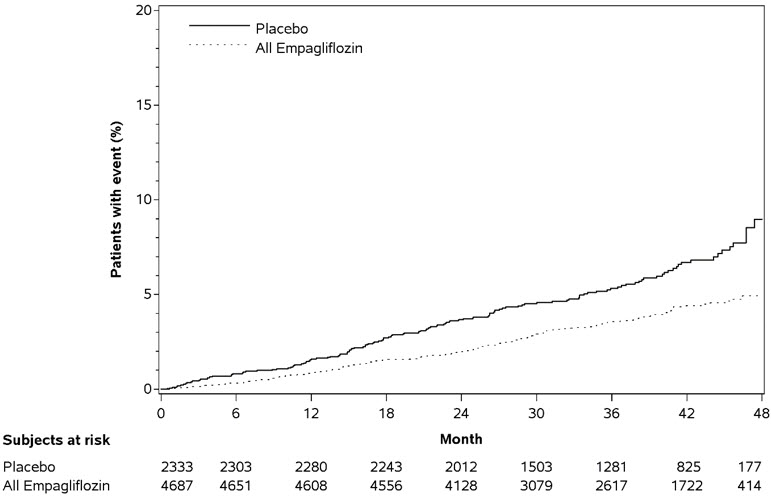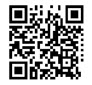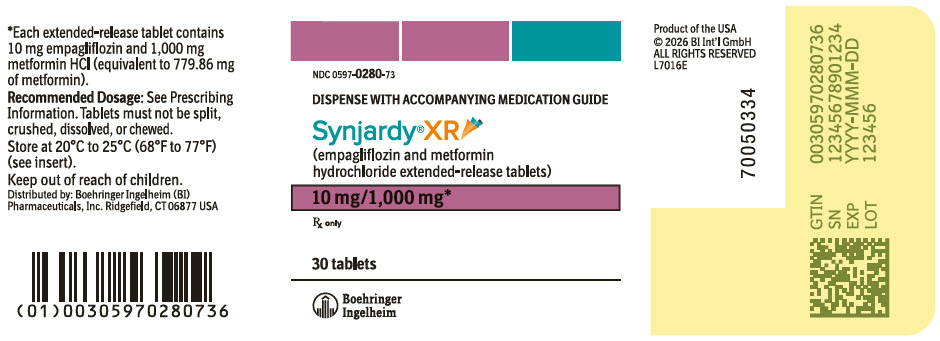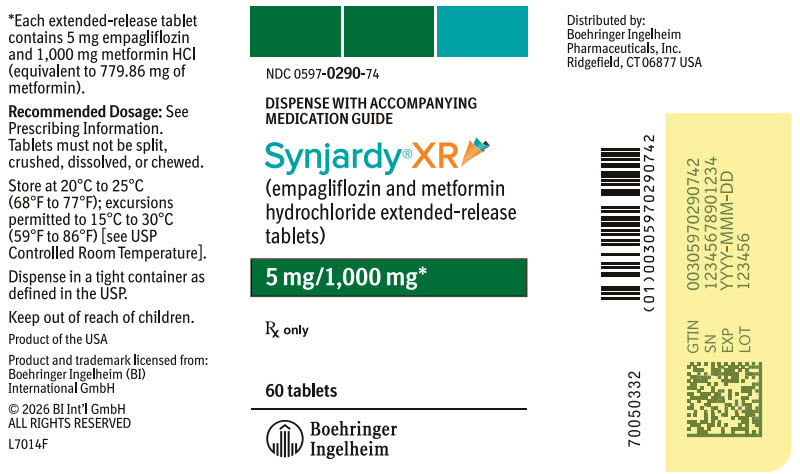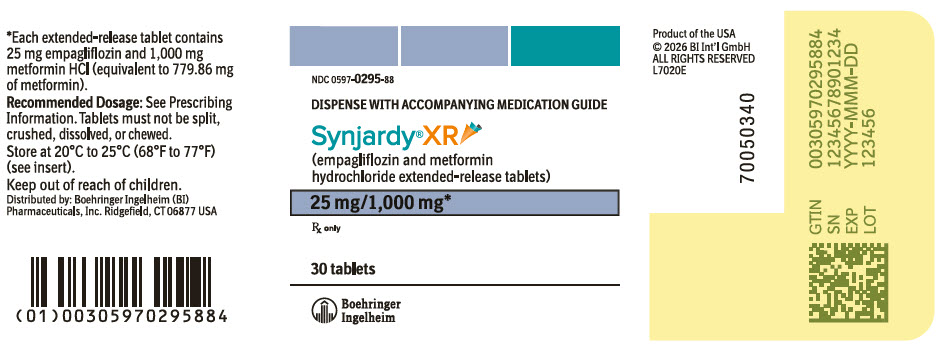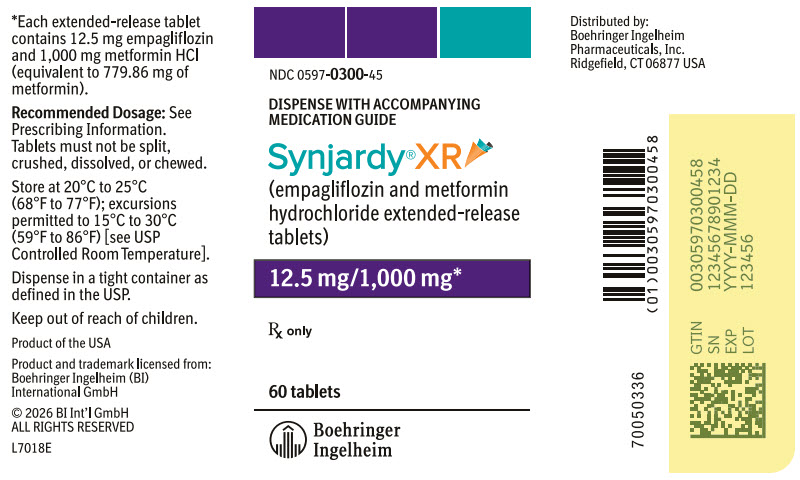 DRUG LABEL: Synjardy
NDC: 0597-0280 | Form: TABLET, EXTENDED RELEASE
Manufacturer: Boehringer Ingelheim Pharmaceuticals, Inc.
Category: prescription | Type: HUMAN PRESCRIPTION DRUG LABEL
Date: 20260120

ACTIVE INGREDIENTS: EMPAGLIFLOZIN 10 mg/1 1; METFORMIN HYDROCHLORIDE 1000 mg/1 1

HIGHLIGHTS OF PRESCRIBING INFORMATION

These highlights do not include all the information needed to use SYNJARDY and SYNJARDY XR safely and effectively. See full prescribing information for SYNJARDY and SYNJARDY XR.
SYNJARDY® (empagliflozin and metformin hydrochloride tablets), for oral use
SYNJARDY® XR (empagliflozin and metformin hydrochloride extended-release tablets), for oral use
Initial U.S. Approval: 2015

WARNING: LACTIC ACIDOSIS

See full prescribing information for complete boxed warning.

- Postmarketing cases of metformin-associated lactic acidosis have resulted in death, hypothermia, hypotension, and resistant bradyarrhythmias. Symptoms included malaise, myalgias, respiratory distress, somnolence, and abdominal pain. Laboratory abnormalities included elevated blood lactate levels, anion gap acidosis, increased lactate/pyruvate ratio; and metformin plasma levels generally >5 mcg/mL. (5.1)
- Risk factors include renal impairment, concomitant use of certain drugs, age ≥65 years old, radiological studies with contrast, surgery and other procedures, hypoxic states, excessive alcohol intake, and hepatic impairment. Steps to reduce the risk of and manage metformin-associated lactic acidosis in these high risk groups are provided in the Full Prescribing Information. (5.1)
- If lactic acidosis is suspected, discontinue SYNJARDY or SYNJARDY XR and institute general supportive measures in a hospital setting. Prompt hemodialysis is recommended. (5.1)

RECENT MAJOR CHANGES

Indications and Usage (1) | 3/2025
Warnings and Precautions, Genitourinary Infections, including Urosepsis, Pyelonephritis, Necrotizing Fasciitis of the Perineum (Fournier's Gangrene), and Genital Mycotic Infections (5.4) | 10/2025
Warnings and Precautions, Lower Limb Amputation (5.6) | 3/2025

1 INDICATIONS AND USAGE

SYNJARDY

SYNJARDY is a combination of empagliflozin, a sodium-glucose co-transporter 2 (SGLT2) inhibitor and metformin hydrochloride (HCl) immediate-release, a biguanide, indicated as an adjunct to diet and exercise to improve glycemic control in adults and pediatric patients aged 10 years and older with type 2 diabetes mellitus.

SYNJARDY XR

SYNJARDY XR is a combination of empagliflozin, a SGLT2 inhibitor and metformin HCl extended-release, a biguanide, indicated as an adjunct to diet and exercise to improve glycemic control in adults with type 2 diabetes mellitus.

Empagliflozin

Empagliflozin, when used as a component of SYNJARDY or SYNJARDY XR, is indicated in adults with type 2 diabetes mellitus to reduce the risk of:

- Cardiovascular (CV) death in adults with established CV disease. (1)
- CV death and hospitalization for heart failure in adults with heart failure. (1)
- Sustained decline in eGFR, end-stage kidney disease, CV death, and hospitalization in adults with chronic kidney disease at risk of progression. (1)

Limitations of Use:

- Not recommended for use to improve glycemic control in patients with type 1 diabetes mellitus. It may increase the risk of diabetic ketoacidosis in these patients. (1)
- Because of the metformin HCl component, the use of SYNJARDY or SYNJARDY XR is limited to patients with type 2 diabetes mellitus for all indications. (1)
- Empagliflozin, when used as a component of SYNJARDY or SYNJARDY XR, is not recommended for the treatment of chronic kidney disease in patients with polycystic kidney disease or patients requiring or with a recent history of intravenous immunosuppressive therapy or greater than 45 mg of prednisone or equivalent for kidney disease. Empagliflozin is not expected to be effective in these populations. (1)

2 DOSAGE AND ADMINISTRATION

- Assess renal function before initiating and as clinically indicated. Assess volume status and correct volume depletion before initiating. (2.1)
- Individualize the starting dosage based on the patient's current regimen and renal function. (2.2, 2.3, 2.4)
- The maximum recommended dosage is 25 mg/day of empagliflozin and 2,000 mg/day of metformin HCl. (2.2, 2.3)
- Initiation of SYNJARDY or SYNJARDY XR is not recommended in patients with an eGFR less than 45 mL/min/1.73 m^2, due to the metformin HCl component. (2.4)
- SYNJARDY: take orally twice daily with meals, with gradual dosage escalation to reduce the gastrointestinal adverse reactions due to metformin HCl. (2.2, 2.3)
- SYNJARDY XR: take orally once daily with a meal in the morning, with gradual dosage escalation to reduce the gastrointestinal adverse reactions due to metformin HCl. Swallow whole; do not split, crush, dissolve, or chew. (2.2)
- SYNJARDY or SYNJARDY XR may need to be discontinued at time of, or prior to, iodinated contrast imaging procedures. (2.5)
- Withhold SYNJARDY or SYNJARDY XR at least 3 days, if possible, prior to surgery or procedures associated with prolonged fasting. (2.6)

3 DOSAGE FORMS AND STRENGTHS

SYNJARDY Tablets:

- 5 mg empagliflozin/500 mg metformin HCl (3)
- 5 mg empagliflozin/1,000 mg metformin HCl (3)
- 12.5 mg empagliflozin/500 mg metformin HCl (3)
- 12.5 mg empagliflozin/1,000 mg metformin HCl (3)

SYNJARDY XR Tablets:

- 5 mg empagliflozin/1,000 mg metformin HCl extended-release (3)
- 10 mg empagliflozin/1,000 mg metformin HCl extended-release (3)
- 12.5 mg empagliflozin/1,000 mg metformin HCl extended-release (3)
- 25 mg empagliflozin/1,000 mg metformin HCl extended-release (3)

4 CONTRAINDICATIONS

- Severe renal impairment (eGFR below 30 mL/min/1.73 m^2) (4)
- Metabolic acidosis, including diabetic ketoacidosis (4)
- Hypersensitivity to empagliflozin, metformin HCl or any of the excipients in SYNJARDY or SYNJARDY XR (4)

5 WARNINGS AND PRECAUTIONS

- Diabetic Ketoacidosis in Patients with Type 1 Diabetes Mellitus and Other Ketoacidosis: Consider ketone monitoring in patients at risk of ketoacidosis, as indicated. Assess for ketoacidosis regardless of presenting blood glucose levels and discontinue SYNJARDY or SYNJARDY XR if ketoacidosis is suspected. Monitor patients for resolution of ketoacidosis before restarting. (5.2)
- Volume Depletion: Before initiating SYNJARDY or SYNJARDY XR, assess volume status and renal function in patients with impaired renal function, elderly patients, or patients on loop diuretics. Monitor for signs and symptoms during therapy. (5.3)
- Genitourinary Infections, including Urosepsis, Pyelonephritis, Necrotizing Fasciitis of the Perineum (Fournier's Gangrene), and Genital Mycotic Infections: Monitor patients for signs and symptoms of genitourinary infections and treat promptly, if indicated. Immediately evaluate patients presenting with pain or tenderness, erythema, or swelling in the genital or perineal area, along with fever or malaise, for necrotizing fasciitis and if suspected, discontinue SYNJARDY or SYNJARDY XR, and promptly institute appropriate medical and/or surgical intervention. (5.4)
- Hypoglycemia: Adult patients taking an insulin secretagogue or insulin may have an increased risk of hypoglycemia. In pediatric patients 10 years of age and older, the risk of hypoglycemia was higher regardless of insulin use. Consider lowering the dosage of insulin secretagogue or insulin to reduce the risk of hypoglycemia when initiating SYNJARDY or SYNJARDY XR. (5.5)
- Lower Limb Amputation: Monitor patients for infections or ulcers of lower limbs, and institute appropriate treatment. (5.6)
- Hypersensitivity Reactions: Serious hypersensitivity reactions (e.g., angioedema) have occurred with empagliflozin. If hypersensitivity reactions occur, discontinue SYNJARDY or SYNJARDY XR, treat promptly, and monitor until signs and symptoms resolve. (5.7)
- Vitamin B12 Deficiency: Metformin may lower vitamin B12 levels. Measure hematologic parameters annually and vitamin B12 at 2 to 3 year intervals and manage any abnormalities. (5.8)

6 ADVERSE REACTIONS

- Most common adverse reactions associated with empagliflozin (5% or greater incidence) were urinary tract infections and female genital mycotic infections. (6.1)
- Most common adverse reactions associated with metformin HCl (>5%) are diarrhea, nausea/vomiting, flatulence, abdominal discomfort, indigestion, asthenia, and headache. (6.1)

To report SUSPECTED ADVERSE REACTIONS, contact Boehringer Ingelheim Pharmaceuticals, Inc. at 1-800-542-6257 or FDA at 1-800-FDA-1088 or www.fda.gov/medwatch.

7 DRUG INTERACTIONS

- Carbonic Anhydrase Inhibitors: May increase risk of lactic acidosis. Consider more frequent monitoring. (7)
- Drugs that Reduce Metformin Clearance: May increase risk of lactic acidosis. Consider benefits and risks of concomitant use. (7)
- See full prescribing information for additional drug interactions and information on interference of SYNJARDY or SYNJARDY XR with laboratory tests. (7)

8 USE IN SPECIFIC POPULATIONS

- Pregnancy: Advise females of the potential risk to a fetus especially during the second and third trimesters. (8.1)
- Lactation: Not recommended when breastfeeding. (8.2)
- Females and Males of Reproductive Potential: Advise premenopausal females of the potential for an unintended pregnancy. (8.3)
- Geriatric Patients: Higher incidence of adverse reactions related to volume depletion and reduced renal function. (8.5)
- Renal Impairment: Higher incidence of adverse reactions related to reduced renal function. (8.6)
- Hepatic Impairment: Avoid use in patients with hepatic impairment. (8.7)

FULL PRESCRIBING INFORMATION

WARNING: LACTIC ACIDOSIS

Postmarketing cases of metformin-associated lactic acidosis have resulted in death, hypothermia, hypotension, and resistant bradyarrhythmias. The onset of metformin-associated lactic acidosis is often subtle, accompanied only by nonspecific symptoms such as malaise, myalgias, respiratory distress, somnolence, and abdominal pain. Metformin-associated lactic acidosis was characterized by elevated blood lactate levels (>5 mmol/Liter), anion gap acidosis (without evidence of ketonuria or ketonemia), an increased lactate/pyruvate ratio; and metformin plasma levels generally >5 mcg/mL [see Warnings and Precautions (5.1)].

Risk factors for metformin-associated lactic acidosis include renal impairment, concomitant use of certain drugs (e.g., carbonic anhydrase inhibitors such as topiramate), age 65 years old or greater, having a radiological study with contrast, surgery and other procedures, hypoxic states (e.g., acute congestive heart failure), excessive alcohol intake, and hepatic impairment.

Steps to reduce the risk of and manage metformin-associated lactic acidosis in these high risk groups are provided in the full prescribing information [see Dosage and Administration (2.1), Contraindications (4), Warnings and Precautions (5.1), Drug Interactions (7), and Use in Specific Populations (8.6, 8.7)].

If metformin-associated lactic acidosis is suspected, immediately discontinue SYNJARDY or SYNJARDY XR and institute general supportive measures in a hospital setting. Prompt hemodialysis is recommended [see Warnings and Precautions (5.1)].

1 INDICATIONS AND USAGE

SYNJARDY

SYNJARDY is a combination of empagliflozin and metformin hydrochloride (HCl) immediate-release indicated as an adjunct to diet and exercise to improve glycemic control in adults and pediatric patients aged 10 years and older with type 2 diabetes mellitus.

SYNJARDY XR

SYNJARDY XR is a combination of empagliflozin and metformin HCl extended-release indicated as an adjunct to diet and exercise to improve glycemic control in adults with type 2 diabetes mellitus.

Empagliflozin

Empagliflozin, when used as a component of SYNJARDY or SYNJARDY XR, is indicated in adults with type 2 diabetes mellitus to reduce the risk of:

• Cardiovascular (CV) death in adults with established CV disease.

• CV death and hospitalization for heart failure in adults with heart failure.

• Sustained decline in eGFR, end-stage kidney disease, CV death, and hospitalization in adults with chronic kidney disease at risk of progression.

Limitations of Use

• SYNJARDY and SYNJARDY XR are not recommended for use to improve glycemic control in patients with type 1 diabetes mellitus. It may increase the risk of diabetic ketoacidosis in these patients [see Warnings and Precautions (5.2)].

• Because of the metformin HCl component, the use of SYNJARDY or SYNJARDY XR is limited to patients with type 2 diabetes mellitus for all indications.

• Empagliflozin, when used as a component of SYNJARDY or SYNJARDY XR, is not recommended for the treatment of chronic kidney disease in patients with polycystic kidney disease or patients requiring or with a recent history of intravenous immunosuppressive therapy or greater than 45 mg of prednisone or equivalent for kidney disease [see Clinical Studies (14.5)]. Empagliflozin is not expected to be effective in these populations.

2 DOSAGE AND ADMINISTRATION

2.1 Testing Prior to Initiation of SYNJARDY or SYNJARDY XR

- Assess renal function before initiating SYNJARDY or SYNJARDY XR and as clinically indicated [see Warnings and Precautions (5.1, 5.3)].
- Assess volume status. In patients with volume depletion, correct this condition before initiating SYNJARDY or SYNJARDY XR [see Warnings and Precautions (5.3) and Use in Specific Populations (8.5, 8.6)].

2.2 Recommended Dosage and Administration of SYNJARDY or SYNJARDY XR in Adults

- When switching to SYNJARDY or SYNJARDY XR from:
  - Metformin HCl: initiate SYNJARDY or SYNJARDY XR at a similar total daily dosage of metformin HCl and a total daily empagliflozin dosage of 10 mg.
  - Empagliflozin: initiate SYNJARDY or SYNJARDY XR at the same total daily dosage of empagliflozin and a total daily metformin HCl dosage of 1,000 mg.
  - Empagliflozin and metformin HCl: initiate SYNJARDY or SYNJARDY XR at the same total daily dosages of each component.
- Recommended dosage of SYNJARDY or SYNJARDY XR:
  - The recommended total daily dosage of empagliflozin is 10 mg.
  - For additional glycemic control, empagliflozin may be increased to a maximum total daily dosage of 25 mg in patients tolerating 10 mg daily and metformin HCl may be increased to a maximum total daily dosage of 2,000 mg, with gradual escalation to reduce gastrointestinal adverse reactions with metformin HCl [see Adverse Reactions (6.1)].
- Take SYNJARDY orally twice daily with meals.
- Take SYNJARDY XR orally once daily with a meal in the morning. Swallow each tablet whole. Do not split, crush, dissolve, or chew.

2.3 Recommended Dosage and Administration of SYNJARDY in Pediatric Patients Aged 10 Years and Older

- Individualize the dosage of SYNJARDY based on the patient's current regimen.
- Monitor effectiveness and tolerability, and adjust dosage as appropriate, not to exceed the maximum total daily dosage of empagliflozin 25 mg and metformin HCl 2,000 mg.
- Take SYNJARDY orally twice daily with meals; with gradual dose escalation to reduce gastrointestinal adverse reactions with metformin HCl [see Adverse Reactions (6.1)].

2.4 Dosage Recommendations in Patients with Renal Impairment

- Initiation of SYNJARDY or SYNJARDY XR is not recommended in patients with an eGFR less than 45 mL/min/1.73 m^2, due to the metformin HCl component.
- SYNJARDY and SYNJARDY XR are contraindicated in patients with an eGFR less than 30 mL/min/1.73 m^2 [see Contraindications (4), Warnings and Precautions (5.1), and Use in Specific Populations (8.6)].

2.5 Discontinuation for Iodinated Contrast Imaging Procedures

Discontinue SYNJARDY or SYNJARDY XR at the time of, or prior to, an iodinated contrast imaging procedure in patients with an eGFR less than 60 mL/min/1.73 m^2; in patients with a history of liver disease, alcoholism or heart failure; or in patients who will be administered intra-arterial iodinated contrast. Re-evaluate eGFR 48 hours after the imaging procedure; restart SYNJARDY or SYNJARDY XR if renal function is stable [see Warnings and Precautions (5.1)].

2.6 Temporary Interruption for Surgery

Withhold SYNJARDY or SYNJARDY XR for at least 3 days, if possible, prior to surgery or procedures associated with prolonged fasting. Resume SYNJARDY or SYNJARDY XR when the patient is clinically stable and has resumed oral intake [see Warnings and Precautions (5.2) and Clinical Pharmacology (12.2)].

2.7 Recommendations Regarding Missed Dose

- If a dose is missed, instruct patients to take the dose as soon as possible.
- Advise patients not to double up the next dose.

3 DOSAGE FORMS AND STRENGTHS

SYNJARDY Tablets:

Empagliflozin Strength | Metformin HCl Strength | Color/Shape | Tablet Markings
5 mg | 500 mg | orange yellow, oval, biconvex, film-coated tablet | Boehringer Ingelheim company symbol and "S5" debossed on one side; the other side is debossed with "500".
5 mg | 1,000 mg | brownish yellow, oval, biconvex, film-coated tablet | Boehringer Ingelheim company symbol and "S5" debossed on one side; the other side is debossed with "1000".
12.5 mg | 500 mg | pale brownish purple, oval, biconvex, film-coated tablet | Boehringer Ingelheim company symbol and "S12" debossed on one side; the other side is debossed with "500".
12.5 mg | 1,000 mg | dark brownish purple, oval, biconvex, film-coated tablet | Boehringer Ingelheim company symbol and "S12" debossed on one side; the other side is debossed with "1000".

SYNJARDY XR Tablets:

Empagliflozin Strength | Metformin HCl Extended - Release Strength | Color/Shape | Tablet Markings
5 mg | 1,000 mg | olive green, oval, biconvex, film-coated tablet | Printed on one side in black ink with the Boehringer Ingelheim company symbol and "S5" on the top line and "1000 M" on the bottom line.
10 mg | 1,000 mg | orange, oval, biconvex, film-coated tablet | Printed on one side in black ink with the Boehringer Ingelheim company symbol and "S10" on the top line and "1000 M" on the bottom line.
12.5 mg | 1,000 mg | blue, oval, biconvex, film-coated tablet | Printed on one side in black ink with the Boehringer Ingelheim company symbol and "S12" on the top line and "1000 M" on the bottom line.
25 mg | 1,000 mg | light green, oval, biconvex, film-coated tablet | Printed on one side in black ink with the Boehringer Ingelheim company symbol and "S25" on the top line and "1000 M" on the bottom line.

4 CONTRAINDICATIONS

SYNJARDY and SYNJARDY XR are contraindicated in patients with:

- severe renal impairment (eGFR less than 30 mL/min/1.73 m^2) [see Warnings and Precautions (5.1) and Use in Specific Populations (8.6)].
- acute or chronic metabolic acidosis, including diabetic ketoacidosis [see Warnings and Precautions (5.1)].
- hypersensitivity to empagliflozin, metformin HCl or any of the excipients in SYNJARDY or SYNJARDY XR, reactions such as angioedema have occurred [see Warnings and Precautions (5.7)].

5 WARNINGS AND PRECAUTIONS

5.1 Lactic Acidosis

There have been postmarketing cases of metformin-associated lactic acidosis, including fatal cases. These cases had a subtle onset and were accompanied by nonspecific symptoms such as malaise, myalgias, abdominal pain, respiratory distress, or increased somnolence; however, hypothermia, hypotension, and resistant bradyarrhythmias have occurred with severe acidosis. Metformin-associated lactic acidosis was characterized by elevated blood lactate concentrations (>5 mmol/Liter), anion gap acidosis (without evidence of ketonuria or ketonemia), and an increased lactate:pyruvate ratio; metformin plasma levels generally >5 mcg/mL. Metformin decreases liver uptake of lactate increasing lactate blood levels which may increase the risk of lactic acidosis, especially in patients at risk.

If metformin-associated lactic acidosis is suspected, general supportive measures should be instituted promptly in a hospital setting, along with immediate discontinuation of SYNJARDY or SYNJARDY XR. In SYNJARDY or SYNJARDY XR-treated patients with a diagnosis or strong suspicion of lactic acidosis, prompt hemodialysis is recommended to correct the acidosis and remove accumulated metformin (metformin is dialyzable, with a clearance of up to 170 mL/minute under good hemodynamic conditions). Hemodialysis has often resulted in reversal of symptoms and recovery.

Educate patients and their families about the symptoms of lactic acidosis and if these symptoms occur instruct them to discontinue SYNJARDY or SYNJARDY XR and report these symptoms to their healthcare provider.

For each of the known and possible risk factors for metformin-associated lactic acidosis, recommendations to reduce the risk of and manage metformin-associated lactic acidosis are provided below:

Renal Impairment: The postmarketing metformin-associated lactic acidosis cases primarily occurred in patients with significant renal impairment. The risk of metformin accumulation and metformin-associated lactic acidosis increases with the severity of renal impairment because metformin is substantially excreted by the kidney. Clinical recommendations based upon the patient's renal function include [see Dosage and Administration (2.4) and Clinical Pharmacology (12.3)]:

- Before initiating SYNJARDY or SYNJARDY XR, obtain an estimated glomerular filtration rate (eGFR).
- SYNJARDY and SYNJARDY XR are contraindicated in patients with an eGFR below 30 mL/min/1.73 m^2 [see Contraindications (4)].
- Obtain an eGFR at least annually in all patients taking SYNJARDY or SYNJARDY XR. In patients at increased risk for the development of renal impairment (e.g., the elderly), renal function should be assessed more frequently.

Drug Interactions: The concomitant use of SYNJARDY or SYNJARDY XR with specific drugs may increase the risk of metformin-associated lactic acidosis: those that impair renal function, result in significant hemodynamic change, interfere with acid-base balance or increase metformin accumulation [see Drug Interactions (7)]. Therefore, consider more frequent monitoring of patients.

Age 65 or Greater: The risk of metformin-associated lactic acidosis increases with the patient's age because elderly patients have a greater likelihood of having hepatic, renal, or cardiac impairment than younger patients. Assess renal function more frequently in elderly patients [see Use in Specific Populations (8.5)].

Radiological Studies with Contrast: Administration of intravascular iodinated contrast agents in metformin-treated patients has led to an acute decrease in renal function and the occurrence of lactic acidosis. Stop SYNJARDY or SYNJARDY XR at the time of, or prior to, an iodinated contrast imaging procedure in patients with an eGFR less than 60 mL/min/1.73 m^2; in patients with a history of hepatic impairment, alcoholism, or heart failure; or in patients who will be administered intra-arterial iodinated contrast. Re-evaluate eGFR 48 hours after the imaging procedure, and restart SYNJARDY or SYNJARDY XR if renal function is stable.

Surgery and Other Procedures: Withholding of food and fluids during surgical or other procedures may increase the risk for volume depletion, hypotension and renal impairment. SYNJARDY or SYNJARDY XR should be temporarily discontinued while patients have restricted food and fluid intake.

Hypoxic States: Several of the postmarketing cases of metformin-associated lactic acidosis occurred in the setting of acute congestive heart failure (particularly when accompanied by hypoperfusion and hypoxemia). Cardiovascular collapse (shock), acute myocardial infarction, sepsis, and other conditions associated with hypoxemia have been associated with lactic acidosis and may also cause prerenal azotemia. When such events occur, discontinue SYNJARDY or SYNJARDY XR.

Excessive Alcohol Intake: Alcohol potentiates the effect of metformin on lactate metabolism and this may increase the risk of metformin-associated lactic acidosis. Warn patients against excessive alcohol intake while receiving SYNJARDY or SYNJARDY XR.

Hepatic Impairment: Patients with hepatic impairment have developed cases of metformin-associated lactic acidosis. This may be due to impaired lactate clearance resulting in higher lactate blood levels. Therefore, avoid use of SYNJARDY or SYNJARDY XR in patients with clinical or laboratory evidence of hepatic disease.

5.2 Diabetic Ketoacidosis in Patients with Type 1 Diabetes Mellitus and Other Ketoacidosis

In patients with type 1 diabetes mellitus, empagliflozin, a component of SYNJARDY or SYNJARDY XR, significantly increases the risk of diabetic ketoacidosis, a life-threatening event, beyond the background rate. In placebo-controlled trials of patients with type 1 diabetes mellitus, the risk of ketoacidosis was markedly increased in patients who received sodium glucose co-transporter 2 (SGLT2) inhibitors compared to patients who received placebo and fatal ketoacidosis has occurred with empagliflozin. SYNJARDY and SYNJARDY XR are not indicated for glycemic control in patients with type 1 diabetes mellitus.

Type 2 diabetes mellitus and pancreatic disorders (e.g., history of pancreatitis or pancreatic surgery) are also risk factors for ketoacidosis. There have been postmarketing reports of fatal events of ketoacidosis in patients with type 2 diabetes mellitus using SGLT2 inhibitors, including SYNJARDY or SYNJARDY XR.

Precipitating conditions for diabetic ketoacidosis or other ketoacidosis include under-insulinization due to insulin dose reduction or missed insulin doses, acute febrile illness, reduced caloric intake, ketogenic diet, surgery, volume depletion, and alcohol abuse.

Signs and symptoms are consistent with dehydration and severe metabolic acidosis and include nausea, vomiting, abdominal pain, generalized malaise, and shortness of breath. Blood glucose levels at presentation may be below those typically expected for diabetic ketoacidosis (e.g., less than 250 mg/dL). Ketoacidosis and glucosuria may persist longer than typically expected. Urinary glucose excretion persists for 3 days after discontinuing SYNJARDY or SYNJARDY XR [see Clinical Pharmacology (12.2)]; however, there have been postmarketing reports of ketoacidosis and/or glucosuria lasting greater than 6 days and some up to 2 weeks after discontinuation of SGLT2 inhibitors.

Consider ketone monitoring in patients at risk for ketoacidosis if indicated by the clinical situation. Assess for ketoacidosis regardless of presenting blood glucose levels in patients who present with signs and symptoms consistent with severe metabolic acidosis. If ketoacidosis is suspected, discontinue SYNJARDY or SYNJARDY XR, promptly evaluate, and treat ketoacidosis, if confirmed. Monitor patients for resolution of ketoacidosis before restarting SYNJARDY or SYNJARDY XR.

Withhold SYNJARDY or SYNJARDY XR, if possible, in temporary clinical situations that could predispose patients to ketoacidosis. Resume SYNJARDY or SYNJARDY XR when the patient is clinically stable and has resumed oral intake [see Dosage and Administration (2.6)].

Educate all patients on the signs and symptoms of ketoacidosis and instruct patients to discontinue SYNJARDY or SYNJARDY XR and seek medical attention immediately if signs and symptoms occur.

5.3 Volume Depletion

Empagliflozin can cause intravascular volume depletion which may sometimes manifest as symptomatic hypotension or acute transient changes in creatinine [see Adverse Reactions (6.1)]. There have been post-marketing reports of acute kidney injury, some requiring hospitalization and dialysis, in patients with type 2 diabetes mellitus receiving SGLT2 inhibitors, including empagliflozin. Patients with impaired renal function (eGFR less than 60 mL/min/1.73 m^2), elderly patients, or patients on loop diuretics may be at increased risk for volume depletion or hypotension. Before initiating SYNJARDY or SYNJARDY XR in patients with one or more of these characteristics, assess volume status and renal function. In patients with volume depletion, correct this condition before initiating SYNJARDY or SYNJARDY XR. Monitor for signs and symptoms of volume depletion, and renal function after initiating therapy.

5.4 Genitourinary Infections, including Urosepsis, Pyelonephritis, Necrotizing Fasciitis of the Perineum (Fournier's Gangrene), and Genital Mycotic Infections

Empagliflozin increases urinary glucose excretion [see Clinical Pharmacology (12.2)] and increases the risk of genitourinary infections including urinary tract infections and genital mycotic infections in both male and female patients [see Adverse Reactions (6.1)].

Serious genitourinary infections, including urosepsis, pyelonephritis, and necrotizing fasciitis of the perineum (Fournier's gangrene, a rare life-threatening infection requiring urgent surgical intervention), have occurred in patients with and without diabetes mellitus receiving SGLT2 inhibitors, including empagliflozin [see Adverse Reactions (6.2)]. Cases have required hospitalization. In patients with Fournier's gangrene, serious outcomes have included multiple surgeries and death. SYNJARDY and SYNJARDY XR are only indicated for use in patients with type 2 diabetes mellitus.

Patients with a history of chronic or recurrent genitourinary infections are more likely to develop genitourinary infections when using SYNJARDY or SYNJARDY XR. Monitor patients for signs and symptoms of genitourinary infections and treat promptly, if indicated.

Immediately evaluate patients presenting with pain or tenderness, erythema, or swelling in the genital or perineal area, along with fever or malaise, for necrotizing fasciitis. If suspected, discontinue SYNJARDY or SYNJARDY XR and promptly institute appropriate medical and/or surgical intervention.

5.5 Hypoglycemia

Insulin and insulin secretagogues are known to cause hypoglycemia. In adult patients, the risk of hypoglycemia may be increased when SYNJARDY or SYNJARDY XR is used in combination with insulin secretagogues (e.g., sulfonylurea) or insulin. In pediatric patients aged 10 years and older, the risk of hypoglycemia was higher with empagliflozin regardless of insulin use [see Adverse Reactions (6.1)].

The risk of hypoglycemia may be lowered by a reduction in the dose of sulfonylurea (or other concomitantly administered insulin secretagogues) or insulin. Inform patients using these concomitant medications and pediatric patients of the risk of hypoglycemia and educate them on the signs and symptoms of hypoglycemia.

5.6 Lower Limb Amputation

In some clinical studies with SGLT2 inhibitors an imbalance in the incidence of lower limb amputation has been observed. Across four empagliflozin outcome trials, lower limb amputation event rates were 4.3 and 5.0 events per 1,000 patient-years in the placebo group and the empagliflozin 10 mg or 25 mg dose group, respectively, with a HR of 1.05 (95% CI) (0.81, 1.36).

In a long-term cardio-renal outcome trial with empagliflozin, in patients with chronic kidney disease, the occurrence of lower limb amputations was reported with event rates of 2.9, and 4.3 events per 1,000 patient-years in the placebo, and empagliflozin 10 mg treatment arms, respectively. Amputation of the toe and mid-foot were most frequent (21 out of 28 empagliflozin 10 mg treated patients with lower limb amputations), and some involving above and below the knee. Some patients had multiple amputations.

Peripheral artery disease, and diabetic foot infection (including osteomyelitis), were the most common precipitating medical events leading to the need for an amputation. The risk of amputation was highest in patients with a baseline history of diabetic foot, peripheral artery disease (including previous amputation) or diabetes.

Counsel patients about the importance of routine preventative foot care. Monitor patients receiving SYNJARDY or SYNJARDY XR for signs and symptoms of diabetic foot infection (including osteomyelitis), new pain or tenderness, sores or ulcers involving the lower limbs, and institute appropriate treatment.

5.7 Hypersensitivity Reactions

There have been postmarketing reports of serious hypersensitivity reactions (e.g., angioedema) in patients treated with empagliflozin. If a hypersensitivity reaction occurs, discontinue SYNJARDY or SYNJARDY XR; treat promptly per standard of care, and monitor until signs and symptoms resolve. SYNJARDY and SYNJARDY XR are contraindicated in patients with hypersensitivity to empagliflozin or any of the excipients in SYNJARDY or SYNJARDY XR [see Contraindications (4)].

5.8 Vitamin B12 Deficiency

In metformin HCl clinical trials of 29-week duration, a decrease to subnormal levels of previously normal serum vitamin B12 levels was observed in approximately 7% of metformin-treated patients. Such decrease, possibly due to interference with B12 absorption from the B12-intrinsic factor complex, may be associated with anemia but appears to be rapidly reversible with discontinuation of metformin or vitamin B12 supplementation. Certain individuals (those with inadequate vitamin B12 or calcium intake or absorption) appear to be predisposed to developing subnormal vitamin B12 levels. Measure hematologic parameters on an annual basis and vitamin B12 at 2 to 3 year intervals in patients on SYNJARDY or SYNJARDY XR and manage any abnormalities [see Adverse Reactions (6.1)].

6 ADVERSE REACTIONS

The following important adverse reactions are described below and elsewhere in the labeling:

- Lactic Acidosis [see Boxed Warning and Warnings and Precautions (5.1)]
- Diabetic Ketoacidosis in Patients with Type 1 Diabetes Mellitus and Other Ketoacidosis [see Warnings and Precautions (5.2)]
- Volume Depletion [see Warnings and Precautions (5.3)]
- Genitourinary Infections, including Urosepsis, Pyelonephritis, Necrotizing Fasciitis of the Perineum (Fournier's Gangrene), and Genital Mycotic Infections [see Warnings and Precautions (5.4)]
- Hypoglycemia [see Warnings and Precautions (5.5)]
- Lower Limb Amputation [see Warnings and Precautions (5.6)]
- Hypersensitivity Reactions [see Warnings and Precautions (5.7)]
- Vitamin B12 Deficiency [see Warnings and Precautions (5.8)]

6.1 Clinical Trials Experience

Because clinical trials are conducted under widely varying conditions, adverse reaction rates observed in the clinical trials of a drug cannot be directly compared to rates in the clinical trials of another drug and may not reflect the rates observed in practice.

The safety of concomitantly administered empagliflozin (daily dosage 10 mg or 25 mg) and metformin HCl (mean daily dosage of approximately 1,800 mg) has been evaluated in 3,456 adult patients with type 2 diabetes mellitus treated for 16 to 24 weeks, of which 926 patients received placebo, 1,271 patients received a daily dosage of empagliflozin 10 mg, and 1,259 patients received a daily dosage of empagliflozin 25 mg. Discontinuation of therapy due to adverse events across treatment groups was 3.0%, 2.8%, and 2.9% for placebo, empagliflozin 10 mg, and empagliflozin 25 mg, respectively.

Adverse Reactions in a Clinical Trial with Empagliflozin (Add-On Combination Therapy with Metformin HCl and Sulfonylurea) for Glycemic Control in Adults with Type 2 Diabetes Mellitus

In a 24-week placebo-controlled trial of empagliflozin 10 mg or 25 mg administered once daily added to metformin HCl and sulfonylurea, adverse reactions reported in ≥5% of empagliflozin-treated patients and more commonly than in placebo-treated patients are presented in Table 1 (see also Table 4).

Table 1 Adverse Reactions Reported in ≥5% of Adults with Type 2 Diabetes Mellitus Treated with Empagliflozin added on to Metformin HCl plus Sulfonylurea and Greater than with Placebo in a 24-week Placebo Controlled Clinical Trial
Adverse Reactions | Placebo (%) n=225 | Empagliflozin 10 mg (%) n=224 | Empagliflozin 25 mg (%) n=217
Hypoglycemia | 9.8 | 15.6 | 12.9
Urinary tract infection | 6.7 | 9.4 | 6.9
Nasopharyngitis | 4.9 | 8.0 | 6.0

Empagliflozin

Clinical Trials in Adults with Type 2 Diabetes Mellitus

The data in Table 2 are derived from a pool of four 24-week placebo-controlled trials and 18-week data from a placebo-controlled trial with basal insulin in adult patients with type 2 diabetes mellitus. Empagliflozin was used as monotherapy in one trial and as add-on therapy in four trials [see Clinical Studies (14.1)].

These data reflect exposure of 1,976 adult patients to empagliflozin with a mean exposure duration of approximately 23 weeks. Patients received placebo (N=995), empagliflozin 10 mg (N=999), or empagliflozin 25 mg (N=977) once daily. The mean age of the population was 56 years and 3% were older than 75 years of age. More than half (55%) of the population was male; 46% were White, 50% were Asian, and 3% were Black or African American. At baseline, 57% of the population had diabetes mellitus more than 5 years and had a mean hemoglobin A1c (HbA1c) of 8%. Established microvascular complications of diabetes mellitus at baseline included diabetic nephropathy (7%), retinopathy (8%), or neuropathy (16%). Baseline renal function was normal or mildly impaired in 91% of patients and moderately impaired in 9% of patients (mean eGFR 86.8 mL/min/1.73 m^2).

Table 2 shows adverse reactions (excluding hypoglycemia) that were not present at baseline, occurred more commonly in empagliflozin-treated patients than placebo-treated patients, and occurred in greater than or equal to 2% of empagliflozin-treated patients.

Table 2 Adverse Reactions Reported in ≥2% of Adults with Type 2 Diabetes Mellitus Treated with Empagliflozin and Greater than Placebo in Pooled Placebo-Controlled Clinical Trials of Empagliflozin Monotherapy or Combination Therapy
Adverse Reactions | Placebo (%) N=995 | Empagliflozin 10 mg (%) N=999 | Empagliflozin 25 mg (%) N=977
Urinary tract infectiona | 7.6 | 9.3 | 7.6
Female genital mycotic infectionsb | 1.5 | 5.4 | 6.4
Upper respiratory tract infection | 3.8 | 3.1 | 4.0
Increased urinationc | 1.0 | 3.4 | 3.2
Dyslipidemia | 3.4 | 3.9 | 2.9
Arthralgia | 2.2 | 2.4 | 2.3
Male genital mycotic infectionsd | 0.4 | 3.1 | 1.6
Nausea | 1.4 | 2.3 | 1.1
aPredefined adverse event grouping, including, but not limited to, urinary tract infection, asymptomatic bacteriuria, cystitis
bFemale genital mycotic infections include the following adverse reactions: vulvovaginal mycotic infection, vaginal infection, vulvitis, vulvovaginal candidiasis, genital infection, genital candidiasis, genital infection fungal, genitourinary tract infection, vulvovaginitis, cervicitis, urogenital infection fungal, vaginitis bacterial. Percentages calculated with the number of female subjects in each group as denominator: placebo (N=481), empagliflozin 10 mg (N=443), empagliflozin 25 mg (N=420).
cPredefined adverse event grouping, including, but not limited to, polyuria, pollakiuria, and nocturia
dMale genital mycotic infections include the following adverse reactions: balanoposthitis, balanitis, genital infections fungal, genitourinary tract infection, balanitis candida, scrotal abscess, penile infection. Percentages calculated with the number of male subjects in each group as denominator: placebo (N=514), empagliflozin 10 mg (N=556), empagliflozin 25 mg (N=557).

Thirst (including polydipsia) was reported in 0%, 1.7%, and 1.5% for placebo, empagliflozin 10 mg, and empagliflozin 25 mg, respectively.

Volume Depletion

Empagliflozin causes an osmotic diuresis, which may lead to intravascular volume contraction and adverse reactions related to volume depletion. In the pool of five placebo-controlled clinical trials in adults, adverse reactions related to volume depletion (e.g., blood pressure (ambulatory) decreased, blood pressure systolic decreased, dehydration, hypotension, hypovolemia, orthostatic hypotension, and syncope) were reported by 0.3%, 0.5%, and 0.3% of patients treated with placebo, empagliflozin 10 mg, and empagliflozin 25 mg, respectively. Empagliflozin may increase the risk of hypotension in patients at risk for volume contraction [see Use in Specific Populations (8.5, 8.6)].

Increased Urination

In the pool of five placebo-controlled clinical trials in adults, adverse reactions of increased urination (e.g., polyuria, pollakiuria, and nocturia) occurred more frequently on empagliflozin than on placebo (see Table 2). Specifically, nocturia was reported by 0.4%, 0.3%, and 0.8% of patients treated with placebo, empagliflozin 10 mg, and empagliflozin 25 mg, respectively.

Hypoglycemia in Clinical Trials with Empagliflozin for Glycemic Control in Adults with Type 2 Diabetes Mellitus

The incidence of hypoglycemia in adults by trial is shown in Table 3. The incidence of hypoglycemia increased when empagliflozin was administered with insulin or sulfonylurea.

Table 3 Incidence of Overalla and Severeb Hypoglycemic Events in Placebo-Controlled Clinical Trials for Glycemic Control in Adults with Type 2 Diabetes Mellitusc
Monotherapy (24 weeks) | Placebo (n=229) | Empagliflozin 10 mg (n=224) | Empagliflozin 25 mg (n=223)
Overall (%) | 0.4 | 0.4 | 0.4
Severe (%) | 0 | 0 | 0
In Combination with Metformin HCl (24 weeks) | Placebo + Metformin HCl (n=206) | Empagliflozin 10 mg + Metformin HCl (n=217) | Empagliflozin 25 mg + Metformin HCl (n=214)
Overall (%) | 0.5 | 1.8 | 1.4
Severe (%) | 0 | 0 | 0
In Combination with Metformin HCl + Sulfonylurea (24 weeks) | Placebo (n=225) | Empagliflozin 10 mg + Metformin HCl + Sulfonylurea (n=224) | Empagliflozin 25 mg + Metformin HCl + Sulfonylurea (n=217)
Overall (%) | 8.4 | 16.1 | 11.5
Severe (%) | 0 | 0 | 0
In Combination with Pioglitazone +/- Metformin HCl (24 weeks) | Placebo (n=165) | Empagliflozin 10 mg + Pioglitazone +/- Metformin HCl (n=165) | Empagliflozin 25 mg + Pioglitazone +/- Metformin HCl (n=168)
Overall (%) | 1.8 | 1.2 | 2.4
Severe (%) | 0 | 0 | 0
In Combination with Basal Insulin +/- Metformin HCl (18 weeksd) | Placebo (n=170) | Empagliflozin 10 mg (n=169) | Empagliflozin 25 mg (n=155)
Overall (%) | 20.6 | 19.5 | 28.4
Severe (%) | 0 | 0 | 1.3
In Combination with MDI Insulin +/- Metformin HCl (18 weeksd) | Placebo (n=188) | Empagliflozin 10 mg (n=186) | Empagliflozin 25 mg (n=189)
Overall (%) | 37.2 | 39.8 | 41.3
Severe (%) | 0.5 | 0.5 | 0.5
aOverall hypoglycemic events: plasma or capillary glucose of less than or equal to 70 mg/dL
bSevere hypoglycemic events: requiring assistance regardless of blood glucose
cTreated set (patients who had received at least one dosage of trial drug)
dInsulin dosage could not be adjusted during the initial 18-week treatment period

Other Adverse Reactions in Clinical Trials with Empagliflozin in Adults

- Genital Mycotic Infections: In the pool of five placebo-controlled clinical trials, the incidence of genital mycotic infections (e.g., vaginal mycotic infection, vaginal infection, genital infection fungal, vulvovaginal candidiasis, and vulvitis) was increased in patients treated with empagliflozin compared to placebo, occurring in 0.9%, 4.1%, and 3.7% of patients randomized to placebo, empagliflozin 10 mg, and empagliflozin 25 mg, respectively. Discontinuation from trial due to genital infection occurred in 0% of placebo-treated patients and 0.2% of patients treated with either empagliflozin 10 mg or 25 mg.
  Genital mycotic infections occurred more frequently in female than male patients (see Table 2).
  Phimosis occurred more frequently in male patients treated with empagliflozin 10 mg (less than 0.1%) and empagliflozin 25 mg (0.1%) than placebo (0%).
- Urinary Tract Infections: In the pool of five placebo-controlled clinical trials, the incidence of urinary tract infections (e.g., urinary tract infection, asymptomatic bacteriuria, and cystitis) was increased in patients treated with empagliflozin compared to placebo (see Table 2). Patients with a history of chronic or recurrent urinary tract infections were more likely to experience a urinary tract infection. The rate of treatment discontinuation due to urinary tract infections was 0.1%, 0.2%, and 0.1% for placebo, empagliflozin 10 mg, and empagliflozin 25 mg, respectively.
  Urinary tract infections occurred more frequently in female patients. The incidence of urinary tract infections in female patients randomized to placebo, empagliflozin 10 mg, and empagliflozin 25 mg was 16.6%, 18.4%, and 17.0%, respectively. The incidence of urinary tract infections in male patients randomized to placebo, empagliflozin 10 mg, and empagliflozin 25 mg was 3.2%, 3.6%, and 4.1%, respectively [see Use in Specific Populations (8.5)].
- Lower Limb Amputations: Across four empagliflozin outcome trials, lower limb amputation event rates were 4.3 and 5.0 events per 1,000 patient-years in the placebo group and the empagliflozin 10 mg or 25 mg dose group, respectively, with a HR of 1.05 (95% CI) (0.81, 1.36). In a long-term cardio-renal outcome trial with empagliflozin, in patients with chronic kidney disease, the occurrence of lower limb amputations was reported with event rates of 2.9, and 4.3 events per 1,000 patient-years in the placebo, and empagliflozin 10 mg treatment arms, respectively.

Clinical Trial of Empagliflozin in Pediatric Patients Aged 10 to 17 Years with Type 2 Diabetes Mellitus

Empagliflozin was administered to 52 patients in a trial of 157 pediatric patients aged 10 to 17 years with type 2 diabetes mellitus with a mean exposure to empagliflozin of 23.8 weeks [see Clinical Studies (14.2)]. Background therapies as adjunct to diet and exercise included metformin HCl (51%), a combination of metformin HCl and insulin (40.1%), insulin (3.2%), or none (5.7%). The mean HbA1c at baseline was 8.0% and the mean duration of type 2 diabetes mellitus was 2.1 years. The mean age was 14.5 years (range: 10-17 years) and 51.6% were aged 15 years and older. Approximately, 50% were White, 6% were Asian, 31% were Black or African American, and 38% were of Hispanic or Latino ethnicity. The mean BMI was 36.0 kg/m^2 and mean BMI Z-score was 3.0. Approximately 25% of the trial population had microalbuminuria or macroalbuminuria.

The risk of hypoglycemia was higher in pediatric patients treated with empagliflozin regardless of concomitant insulin use. Hypoglycemia, defined as a blood glucose <54 mg/dL, occurred in 10 (19.2%) patients and in 4 (7.5%) patients treated with empagliflozin and placebo, respectively. No severe hypoglycemic events occurred (severe hypoglycemia was defined as an event requiring the assistance of another person to actively administer carbohydrates, glucagon or take other corrective actions).

Adverse Reactions with Clinical Trials of Metformin HCl

The most common (>5%) established adverse reactions due to initiation of metformin HCl therapy are diarrhea, nausea/vomiting, flatulence, abdominal discomfort, indigestion, asthenia, and headache.

In a 24-week clinical trial in which extended-release metformin HCl or placebo was added to glyburide therapy, the most common (>5% and greater than placebo) adverse reactions in the combined treatment group were hypoglycemia (13.7% vs 4.9%), diarrhea (12.5% vs 5.6%), and nausea (6.7% vs 4.2%).

Pediatric Patients

In clinical trials with metformin HCl immediate-release tablets in pediatric patients with type 2 diabetes mellitus, the profile of adverse reactions was similar to that observed in adults.

Laboratory Test Abnormalities in Clinical Trials of Empagliflozin or Metformin HCl

Empagliflozin

- Increases in Serum Creatinine and Decreases in eGFR: Initiation of empagliflozin causes an increase in serum creatinine and decrease in eGFR within weeks of starting therapy and then these changes stabilize. In a trial of adults with moderate renal impairment, larger mean changes were observed. In a long-term CV outcomes trial, the increase in serum creatinine and decrease in eGFR generally did not exceed 0.1 mg/dL and -9.0 mL/min/1.73 m^2, respectively, at Week 4, and reversed after treatment discontinuation, suggesting acute hemodynamic changes may play a role in the renal function changes observed with empagliflozin.
- Increase in Low-Density Lipoprotein Cholesterol (LDL-C): Dose-related increases in low-density lipoprotein cholesterol (LDL-C) were observed in adults treated with empagliflozin. LDL-C increased by 2.3%, 4.6%, and 6.5% in patients treated with placebo, empagliflozin 10 mg, and empagliflozin 25 mg, respectively. The range of mean baseline LDL-C levels was 90.3 to 90.6 mg/dL across treatment groups.
- Increase in Hematocrit: In a pool of four placebo-controlled trials in adults, median hematocrit decreased by 1.3% in placebo and increased by 2.8% in empagliflozin 10 mg and 2.8% in empagliflozin 25 mg treated patients. At the end of treatment, 0.6%, 2.7%, and 3.5% of patients with hematocrits initially within the reference range had values above the upper limit of the reference range with placebo, empagliflozin 10 mg, and empagliflozin 25 mg, respectively.

Metformin HCl

- Decrease in Vitamin B12: In metformin HCl clinical trials of 29-week duration, a decrease to subnormal levels of previously normal serum vitamin B12 levels was observed in approximately 7% of patients.

6.2 Postmarketing Experience

Additional adverse reactions have been identified during postapproval use. Because these reactions are reported voluntarily from a population of uncertain size, it is generally not possible to reliably estimate their frequency or establish a causal relationship to drug exposure.

Empagliflozin

Gastrointestinal Disorders: Constipation
Infections: Necrotizing fasciitis of the perineum (Fournier's gangrene), urosepsis and pyelonephritis
Metabolism and Nutrition Disorders: Ketoacidosis
Renal and Urinary Disorders: Acute kidney injury
Skin and Subcutaneous Tissue Disorders: Angioedema, skin reactions (e.g., rash, urticaria)

Metformin HCl

Hepatobiliary Disorders: Cholestatic, hepatocellular, and mixed hepatocellular liver injury

7 DRUG INTERACTIONS

See Table 4 for clinically relevant interactions with SYNJARDY or SYNJARDY XR.

Table 4 Clinically Relevant Interactions with SYNJARDY or SYNJARDY XR
Carbonic Anhydrase Inhibitors
Clinical Impact | Topiramate or other carbonic anhydrase inhibitors (e.g., zonisamide, acetazolamide or dichlorphenamide) frequently causes a decrease in serum bicarbonate and induce non-anion gap, hyperchloremic metabolic acidosis. Concomitant use of these drugs with SYNJARDY or SYNJARDY XR may increase the risk of lactic acidosis.
Intervention | Consider more frequent monitoring of these patients.
Drugs that Reduce Metformin Clearance
Clinical Impact | Concomitant use of drugs that interfere with common renal tubular transport systems involved in the renal elimination of metformin (e.g., organic cationic transporter-2 [OCT2] / multidrug and toxin extrusion [MATE] inhibitors such as ranolazine, vandetanib, dolutegravir, and cimetidine) could increase systemic exposure to metformin and may increase the risk for lactic acidosis [see Clinical Pharmacology (12.3)].
Intervention | Consider the benefits and risks of concomitant use.
Alcohol
Clinical Impact | Alcohol is known to potentiate the effect of metformin on lactate metabolism.
Intervention | Warn patients against excessive alcohol intake while receiving SYNJARDY or SYNJARDY XR.
Diuretics
Clinical Impact | Coadministration of empagliflozin with diuretics resulted in increased urine volume and frequency of voids, which might enhance the potential for volume depletion.
Intervention | Before initiating SYNJARDY or SYNJARDY XR, assess volume status and renal function. In patients with volume depletion, correct this condition before initiating SYNJARDY or SYNJARDY XR. Monitor for signs and symptoms of volume depletion, and renal function after initiating therapy.
Insulin or Insulin Secretagogues
Clinical Impact | The risk of hypoglycemia is increased when SYNJARDY or SYNJARDY XR is used in combination with insulin secretagogues (e.g., sulfonylurea) or insulin.
Intervention | Coadministration of SYNJARDY or SYNJARDY XR with an insulin secretagogue (e.g., sulfonylurea) or insulin may require lower dosages of the insulin secretagogue or insulin to reduce the risk of hypoglycemia.
Drugs Affecting Glycemic Control
Clinical Impact | Certain drugs tend to produce hyperglycemia and may lead to loss of glycemic control. These drugs include the thiazides and other diuretics, corticosteroids, phenothiazines, thyroid products, estrogens, oral contraceptives, phenytoin, nicotinic acid, sympathomimetics, calcium channel blocking drugs, and isoniazid.
Intervention | When such drugs are administered to a patient receiving SYNJARDY or SYNJARDY XR, the patient should be closely observed to maintain adequate glycemic control. When such drugs are withdrawn from a patient receiving SYNJARDY or SYNJARDY XR, the patient should be observed closely for hypoglycemia.
Lithium
Clinical Impact | Concomitant use of an SGLT2 inhibitor with lithium may decrease serum lithium concentrations.
Intervention | Monitor serum lithium concentration more frequently during SYNJARDY or SYNJARDY XR initiation and dosage changes.
Positive Urine Glucose Test
Clinical Impact | SGLT2 inhibitors increase urinary glucose excretion and will lead to positive urine glucose tests.
Intervention | Monitoring glycemic control with urine glucose tests is not recommended in patients taking SGLT2 inhibitors. Use alternative methods to monitor glycemic control.
Interference with 1,5-anhydroglucitol (1,5-AG) Assay
Clinical Impact | Measurements of 1,5-AG are unreliable in assessing glycemic control in patients taking SGLT2 inhibitors.
Intervention | Monitoring glycemic control with 1,5-AG assay is not recommended. Use alternative methods to monitor glycemic control.

8 USE IN SPECIFIC POPULATIONS

8.1 Pregnancy

Risk Summary

Based on animal data showing adverse renal effects from empagliflozin, SYNJARDY and SYNJARDY XR are not recommended during the second and third trimesters of pregnancy.

The limited available data with SYNJARDY, SYNJARDY XR, or empagliflozin in pregnant women are not sufficient to determine a drug-associated risk for major birth defects and miscarriage. Published studies with metformin HCl use during pregnancy have not reported a clear association with metformin HCl and major birth defect or miscarriage risk (see Data). There are risks to the mother and fetus associated with poorly controlled diabetes in pregnancy (see Clinical Considerations).

In animal studies, empagliflozin, a component of SYNJARDY and SYNJARDY XR, resulted in adverse renal changes in rats when administered during a period of renal development corresponding to the late second and third trimesters of human pregnancy. Doses approximately 13-times the maximum clinical dose caused renal pelvic and tubule dilatations that were reversible. No adverse developmental effects were observed when metformin HCl was administered to pregnant rats or rabbits (see Data).

The estimated background risk of major birth defects is 6% to 10% in women with pre-gestational diabetes with a HbA1c >7 and has been reported to be as high as 20% to 25% in women with HbA1c >10. The estimated background risk of miscarriage for the indicated population is unknown. In the U.S. general population, the estimated background risk of major birth defects and miscarriage in clinically recognized pregnancies is 2% to 4% and 15% to 20%, respectively.

Clinical Considerations

Disease-associated maternal and/or embryo/fetal risk

Poorly controlled diabetes in pregnancy increases the maternal risk for diabetic ketoacidosis, pre-eclampsia, spontaneous abortions, preterm delivery, and delivery complications. Poorly controlled diabetes increases the fetal risk for major birth defects, stillbirth, and macrosomia related morbidity.

Data

Human Data

Published data from postmarketing studies have not reported a clear association with metformin HCl and major birth defects, miscarriage, or adverse maternal or fetal outcomes when metformin HCl was used during pregnancy. However, these studies cannot definitely establish the absence of any metformin-associated risk because of methodological limitations, including small sample size and inconsistent comparator groups.

Animal Data

Empagliflozin: Empagliflozin dosed directly to juvenile rats from postnatal day (PND) 21 until PND 90 at doses of 1, 10, 30, and 100 mg/kg/day caused increased kidney weights and renal tubular and pelvic dilatation at 100 mg/kg/day, which approximates 13-times the maximum clinical dose of 25 mg, based on AUC. These findings were not observed after a 13-week, drug-free recovery period. These outcomes occurred with drug exposure during periods of renal development in rats that correspond to the late second and third trimester of human renal development.

In embryo-fetal development studies in rats and rabbits, empagliflozin was administered for intervals coinciding with the first trimester period of organogenesis in humans. Doses up to 300 mg/kg/day, which approximates 48-times (rats) and 128-times (rabbits) the maximum clinical dose of 25 mg (based on AUC), did not result in adverse developmental effects. In rats, at higher doses of empagliflozin causing maternal toxicity, malformations of limb bones increased in fetuses at 700 mg/kg/day or 154-times the 25 mg maximum clinical dose. Empagliflozin crosses the placenta and reaches fetal tissues in rats. In the rabbit, higher doses of empagliflozin resulted in maternal and fetal toxicity at 700 mg/kg/day, or 139-times the 25 mg maximum clinical dose.

In pre- and postnatal development studies in pregnant rats, empagliflozin was administered from gestation day 6 through to lactation day 20 (weaning) at up to 100 mg/kg/day (approximately 16-times the 25 mg maximum clinical dose) without maternal toxicity. Reduced body weight was observed in the offspring at greater than or equal to 30 mg/kg/day (approximately 4-times the 25 mg maximum clinical dose).

Metformin HCl: Metformin HCl did not cause adverse developmental effects when administered to pregnant Sprague Dawley rats and rabbits at doses up to 600 mg/kg/day during the period of organogenesis. This represents an exposure of approximately 2- and 6-times a clinical dose of 2,000 mg, based on body surface area (mg/m^2) for rats and rabbits, respectively.

Empagliflozin and Metformin HCl: No adverse developmental effects were observed when empagliflozin and metformin HCl were coadministered to pregnant rats during the period of organogenesis at exposures of approximately 35- and 14-times the clinical AUC exposure of empagliflozin associated with the 10 mg and 25 mg doses, respectively, and 4-times the clinical AUC exposure of metformin HCl associated with the 2,000 mg dose.

8.2 Lactation

Risk Summary

There is limited information regarding the presence of SYNJARDY, SYNJARDY XR, or its components (empagliflozin or metformin HCl) in human milk, the effects on the breastfed infant, or the effects on milk production. Limited published studies report that metformin is present in human milk (see Data). Empagliflozin is present in the milk of lactating rats (see Data). Since human kidney maturation occurs in utero and during the first 2 years of life when lactational exposure may occur, there may be risk to the developing human kidney.

Because of the potential for serious adverse reactions in a breastfed infant, including the potential for empagliflozin to affect postnatal renal development, advise patients that use of SYNJARDY or SYNJARDY XR is not recommended while breastfeeding.

Data

Published clinical lactation studies report that metformin is present in human milk which resulted in infant doses approximately 0.11% to 1% of the maternal weight-adjusted dosage and a milk/plasma ratio ranging between 0.13 and 1. However, the studies were not designed to definitely establish the risk of use of metformin HCl during lactation because of small sample size and limited adverse event data collected in infants.

Empagliflozin was present at a low level in rat fetal tissues after a single oral dose to the dams at gestation day 18. In rat milk, the mean milk to plasma ratio ranged from 0.634 to 5, and was greater than one from 2 to 24 hours post-dose. The mean maximal milk to plasma ratio of 5 occurred at 8 hours post-dose, suggesting accumulation of empagliflozin in the milk. Juvenile rats directly exposed to empagliflozin showed a risk to the developing kidney (renal pelvic and tubular dilatations) during maturation.

8.3 Females and Males of Reproductive Potential

Discuss the potential for unintended pregnancy with premenopausal women as therapy with metformin HCl may result in ovulation in some anovulatory women.

8.4 Pediatric Use

SYNJARDY

The safety and effectiveness of SYNJARDY as an adjunct to diet and exercise to improve glycemic control in type 2 diabetes mellitus have been established in pediatric patients aged 10 years and older. Use of SYNJARDY for this indication is supported by evidence from a 26-week double-blind, placebo-controlled clinical trial of empagliflozin, with a double-blind active treatment safety extension period of up to 52 weeks in 157 pediatric patients aged 10 to 17 years with type 2 diabetes mellitus and a pediatric pharmacokinetic study [see Clinical Pharmacology (12.3) and Clinical Studies (14.2)].

The safety profile of pediatric patients treated with empagliflozin was similar to that observed in adults with type 2 diabetes mellitus, with the exception of hypoglycemia risk which was higher in pediatric patients treated with empagliflozin regardless of concomitant insulin use [see Warnings and Precautions (5.5) and Adverse Reactions (6.1)].

Use of SYNJARDY for this indication is also supported by evidence from adequate and well-controlled studies of metformin HCl immediate-release tablets in adults with additional data from a controlled clinical study using metformin HCl immediate-release tablets in pediatric patients 10 to 16 years old with type 2 diabetes mellitus [see Clinical Studies (14)]. In this study, adverse reactions were similar to those described in adults.

The safety and effectiveness of SYNJARDY have not been established in pediatric patients less than 10 years of age.

SYNJARDY XR

Safety and effectiveness of SYNJARDY XR have not been established in pediatric patients.

8.5 Geriatric Use

Assess renal function more frequently in SYNJARDY or SYNJARDY XR-treated geriatric patients because there is a greater risk of empagliflozin-associated intravascular volume contraction and symptomatic hypotension in geriatric patients and there is a greater risk of metformin-associated lactic acidosis in geriatric patients [see Dosage and Administration (2.4) and Warnings and Precautions (5.1, 5.3)].

The recommended dosage for the metformin HCl component of SYNJARDY or SYNJARDY XR in geriatric patients should usually start at the lower end of the dosage range.

Empagliflozin

In empagliflozin type 2 diabetes mellitus trials, 2,721 empagliflozin-treated patients were 65 years of age and older and 491 patients were 75 years of age and older. In these trials, volume depletion-related adverse reactions occurred in 2.1%, 2.3%, and 4.4% of patients 75 years of age and older in the placebo, empagliflozin 10 mg, and empagliflozin 25 mg once daily groups, respectively; and urinary tract infections occurred in 10.5%, 15.7%, and 15.1% of patients 75 years of age and older in the placebo, empagliflozin 10 mg, and empagliflozin 25 mg once daily groups, respectively.

In the EMPEROR-Reduced, EMPEROR-Preserved, and EMPA-KIDNEY trials, no overall differences in safety and effectiveness have been observed between patients 65 years of age and older and younger adult patients. EMPEROR-Reduced included 1,188 (64%) patients treated with empagliflozin 65 years of age and older, and 503 (27%) patients 75 years of age and older. EMPEROR-Preserved included 2,403 (80%) patients treated with empagliflozin 65 years of age and older, and 1,281 (43%) patients 75 years of age and older. EMPA-KIDNEY included 1,803 (55%) patients treated with empagliflozin 65 years of age and older, and 758 (23%) patients 75 years of age and older.

Metformin HCl

Clinical studies of metformin HCl did not include sufficient numbers of patients 65 years of age and older to determine whether they respond differently from younger adult patients.

8.6 Renal Impairment

SYNJARDY or SYNJARDY XR should not be initiated in patients with an eGFR less than 45 mL/min/1.73 m^2 due to the metformin HCl component and is contraindicated in patients with severe renal impairment (eGFR less than 30 mL/min/1.73 m^2).

Empagliflozin

The glucose lowering benefit of empagliflozin 25 mg decreased in adult patients with worsening renal function. The risks of renal impairment, volume depletion adverse reactions and urinary tract infection-related adverse reactions increased with worsening renal function [see Warnings and Precautions (5.3)]. In the trial of pediatric patients aged 10 to 17 years with type 2 diabetes mellitus, patients with an eGFR less than 60 mL/min/1.73 m^2 were not enrolled.

Metformin HCl

Metformin is substantially excreted by the kidney, and the risk of metformin accumulation and lactic acidosis increases with the degree of renal impairment [see Warnings and Precautions (5.1)].

8.7 Hepatic Impairment

Use of metformin HCl in patients with hepatic impairment has been associated with some cases of lactic acidosis. SYNJARDY and SYNJARDY XR are not recommended in patients with hepatic impairment [see Warnings and Precautions (5.1)].

10 OVERDOSAGE

In the event of an overdose with SYNJARDY or SYNJARDY XR, consider contacting the Poison Help line (1-800-222-1222) or a medical toxicologist for additional overdosage management recommendations.

Overdose of metformin HCl has occurred, including ingestion of amounts greater than 50 grams. Lactic acidosis has been reported in approximately 32% of metformin overdose cases [see Warnings and Precautions (5.1)]. Metformin is dialyzable with a clearance of up to 170 mL/min under good hemodynamic conditions. Therefore, hemodialysis may be useful for removal of accumulated drug from patients in whom metformin overdosage is suspected.

Removal of empagliflozin by hemodialysis has not been studied.

11 DESCRIPTION

SYNJARDY and SYNJARDY XR tablets for oral use contain: empagliflozin and metformin HCl.

Empagliflozin

Empagliflozin is an inhibitor of the SGLT2.

The chemical name of empagliflozin is D-Glucitol,1,5-anhydro-1-C-[4-chloro-3-[[4-[[(3S)-tetrahydro-3-furanyl]oxy]phenyl]methyl]phenyl]-, (1S).

Its molecular formula is C23H27ClO7 and the molecular weight is 450.91. The structural formula is:

Empagliflozin is a white to yellowish, non-hygroscopic powder. It is very slightly soluble in water, sparingly soluble in methanol, slightly soluble in ethanol and acetonitrile, soluble in 50% acetonitrile/water, and practically insoluble in toluene.

Metformin HCl

Metformin HCl (N,N-dimethylimidodicarbonimidic diamide HCl) is a biguanide. Metformin HCl is a white to off-white crystalline compound with a molecular formula of C4H11N5•HCl and a molecular weight of 165.63. Metformin HCl is freely soluble in water and is practically insoluble in acetone, ether, and chloroform. The pKa of metformin is 12.4. The pH of a 1% aqueous solution of metformin HCl is 6.68. The structural formula is:

SYNJARDY

SYNJARDY tablets for oral administration are available in four dosage strengths containing:

- 5 mg empagliflozin and 500 mg metformin HCl (equivalent to 389.93 mg of metformin)
- 5 mg empagliflozin and 1,000 mg metformin HCl (equivalent to 779.86 mg of metformin)
- 12.5 mg empagliflozin and 500 mg metformin HCl (equivalent to 389.93 mg of metformin)
- 12.5 mg empagliflozin and 1,000 mg metformin HCl (equivalent to 779.86 mg of metformin)

Each film-coated tablet of SYNJARDY contains the following inactive ingredients: colloidal silicon dioxide, copovidone, corn starch, and magnesium stearate. Film-coating: black ferrosoferric oxide and ferric oxide red (12.5 mg/500 mg, 12.5 mg/1,000 mg) or ferric oxide yellow (5 mg/500 mg, 5 mg/1,000 mg), hypromellose, polyethylene glycol 400, talc and titanium dioxide.

SYNJARDY XR

Each film-coated tablet of SYNJARDY XR consists of an extended-release metformin HCl core tablet that is coated with the immediate-release drug substance empagliflozin.

SYNJARDY XR tablets for oral administration are available in four dosage strengths containing:

- 5 mg empagliflozin and 1,000 mg metformin HCl (equivalent to 779.86 mg of metformin)
- 10 mg empagliflozin and 1,000 mg metformin HCl (equivalent to 779.86 mg of metformin)
- 12.5 mg empagliflozin and 1,000 mg metformin HCl (equivalent to 779.86 mg of metformin)
- 25 mg empagliflozin and 1,000 mg metformin HCl (equivalent to 779.86 mg of metformin)

Each film-coated tablet of SYNJARDY XR contains the following inactive ingredients: Tablet Core: hypromellose, magnesium stearate, and polyethylene oxide. Film-coatings and Printing Ink: carnauba wax, FD&C blue#2/indigo carmine aluminum lake (12.5 mg/1,000 mg, 25 mg/1,000 mg), ferric oxide red (10 mg/1,000 mg), ferric oxide yellow (5 mg/1,000 mg, 10 mg/1,000 mg, 25 mg/1,000 mg), ferrosoferric oxide, hypromellose, isopropyl alcohol, polydextrose, polyethylene glycol, propylene glycol, purified water, talc, and titanium dioxide.

12 CLINICAL PHARMACOLOGY

12.1 Mechanism of Action

SYNJARDY or SYNJARDY XR

SYNJARDY and SYNJARDY XR contain: empagliflozin, a SGLT2 inhibitor, and metformin HCl, a biguanide.

Empagliflozin

Empagliflozin is an inhibitor of SGLT2, the predominant transporter responsible for reabsorption of glucose from the glomerular filtrate back into the circulation. By inhibiting SGLT2, empagliflozin reduces renal reabsorption of filtered glucose and lowers the renal threshold for glucose, and thereby increases urinary glucose excretion.

Empagliflozin also reduces sodium reabsorption and increases the delivery of sodium to the distal tubule. This may influence several physiological functions including, but not restricted to, increasing tubuloglomerular feedback and reducing intraglomerular pressure, lowering both pre- and afterload of the heart and downregulating sympathetic activity.

Metformin HCl

Metformin HCl is an antihyperglycemic agent which improves glucose tolerance in patients with type 2 diabetes mellitus, lowering both basal and postprandial plasma glucose. It is not chemically or pharmacologically related to any other classes of oral antihyperglycemic agents. Metformin HCl decreases hepatic glucose production, decreases intestinal absorption of glucose, and improves insulin sensitivity by increasing peripheral glucose uptake and utilization. Unlike sulfonylureas, metformin HCl does not produce hypoglycemia in either patients with type 2 diabetes mellitus or normal subjects (except in special circumstances) [see Warnings and Precautions (5.5)] and does not cause hyperinsulinemia. With metformin HCl therapy, insulin secretion remains unchanged while fasting insulin levels and day-long plasma insulin response may decrease.

12.2 Pharmacodynamics

Empagliflozin

Urinary Glucose Excretion

In patients with type 2 diabetes mellitus, urinary glucose excretion increased immediately following a dose of empagliflozin and was maintained at the end of a 4-week treatment period averaging at approximately 64 grams per day with 10 mg empagliflozin and 78 grams per day with 25 mg empagliflozin once daily [see Clinical Studies (14)]. Data from single oral doses of empagliflozin in healthy subjects indicate that, on average, the elevation in urinary glucose excretion approaches baseline by about 3 days for the 10 mg and 25 mg doses.

Urinary Volume

In a 5-day study, mean 24-hour urine volume increase from baseline was 341 mL on Day 1 and 135 mL on Day 5 of empagliflozin 25 mg once daily treatment.

Cardiac Electrophysiology

In a randomized, placebo-controlled, active-comparator, crossover study, 30 healthy subjects were administered a single oral dose of empagliflozin 25 mg, empagliflozin 200 mg (8 times the maximum dose), moxifloxacin, and placebo. No increase in QTc was observed with either 25 mg or 200 mg empagliflozin.

12.3 Pharmacokinetics

SYNJARDY

Administration of 12.5 mg empagliflozin/1,000 mg metformin HCl under fed conditions resulted in a 9% decrease in AUC and a 28% decrease in Cmax for empagliflozin, when compared to fasted conditions. For metformin, AUC decreased by 12% and Cmax decreased by 26% compared to fasting conditions. The observed effect of food on empagliflozin and metformin is not considered to be clinically relevant.

SYNJARDY XR

Administration of SYNJARDY XR with food resulted in no change in overall exposure of empagliflozin. For metformin HCl extended-release high-fat meals increased systemic exposure to metformin (as measured by area-under-the-curve [AUC]) by approximately 70% relative to fasting, while Cmax is not affected. Meals prolonged Tmax by approximately 3 hours.

Empagliflozin

The pharmacokinetics of empagliflozin has been characterized in healthy volunteers and patients with type 2 diabetes mellitus and no clinically relevant differences were noted between the two populations. The steady-state mean plasma AUC and Cmax were 1,870 nmol∙h/L and 259 nmol/L, respectively, with 10 mg empagliflozin once daily treatment, and 4,740 nmol∙h/L and 687 nmol/L, respectively, with 25 mg empagliflozin once daily treatment. Systemic exposure of empagliflozin increased in a dose-proportional manner in the therapeutic dose range. Empagliflozin does not appear to have time-dependent pharmacokinetic characteristics. Following once-daily dosing, up to 22% accumulation, with respect to plasma AUC, was observed at steady-state.

Absorption

After oral administration, peak plasma concentrations of empagliflozin were reached at 1.5 hours post-dose. Administration of 25 mg empagliflozin after intake of a high-fat and high-calorie meal resulted in slightly lower exposure; AUC decreased by approximately 16% and Cmax decreased by approximately 37%, compared to fasted condition. The observed effect of food on empagliflozin pharmacokinetics was not considered clinically relevant and empagliflozin may be administered with or without food.

Distribution

The apparent steady-state volume of distribution was estimated to be 73.8 L based on a population pharmacokinetic analysis. Following administration of an oral [^14C]-empagliflozin solution to healthy subjects, the red blood cell partitioning was approximately 36.8% and plasma protein binding was 86.2%.

Elimination

The apparent terminal elimination half-life of empagliflozin was estimated to be 12.4 h and apparent oral clearance was 10.6 L/h based on the population pharmacokinetic analysis.

Metabolism

No major metabolites of empagliflozin were detected in human plasma and the most abundant metabolites were three glucuronide conjugates (2-O-, 3-O-, and 6-O-glucuronide). Systemic exposure of each metabolite was less than 10% of total drug-related material. In vitro studies suggested that the primary route of metabolism of empagliflozin in humans is glucuronidation by the uridine 5'-diphospho-glucuronosyltransferases UGT2B7, UGT1A3, UGT1A8, and UGT1A9.

Excretion

Following administration of an oral [^14C]-empagliflozin solution to healthy subjects, approximately 95.6% of the drug-related radioactivity was eliminated in feces (41.2%) or urine (54.4%). The majority of drug-related radioactivity recovered in feces was unchanged parent drug and approximately half of drug-related radioactivity excreted in urine was unchanged parent drug.

Metformin HCl

Absorption

The absolute bioavailability of a metformin HCl 500 mg tablet given under fasting conditions is approximately 50% to 60%. Studies using single oral doses of metformin HCl tablets 500 mg to 1,500 mg, and 850 mg to 2,550 mg, indicate that there is a lack of dose proportionality with increasing doses, which is due to decreased absorption rather than an alteration in elimination.

Food decreases the extent of and slightly delays the absorption of metformin, as shown by approximately a 40% lower Cmax, a 25% lower AUC, and a 35 minute prolongation of time to peak plasma concentration (Tmax) following administration of a single 850 mg tablet of metformin with food, compared to the same tablet strength administered fasting. The clinical relevance of these decreases is unknown.

Metformin HCl extended-release

Following a single oral dose of 1,000 mg (2 × 500 mg tablets) metformin HCl extended-release after a meal, the time to reach maximum plasma metformin concentration (Tmax) is achieved at approximately 7 to 8 hours. In both single- and multiple-dose studies in healthy subjects, once daily 1,000 mg (2 × 500 mg tablets) dosing provides equivalent systemic exposure, as measured by AUC, and up to 35% higher Cmax of metformin relative to the immediate-release given as 500 mg twice daily.

Single oral doses of metformin HCl extended-release from 500 mg to 2,500 mg resulted in less than proportional increase in both AUC and Cmax. Low-fat and high-fat meals increased the systemic exposure (as measured by AUC) from metformin extended-release tablets by about 38% and 73%, respectively, relative to fasting. Both meals prolonged metformin Tmax by approximately 3 hours but Cmax was not affected.

Distribution

The apparent volume of distribution (V/F) of metformin following single oral doses of immediate-release metformin HCl tablets 850 mg averaged 654±358 L. Metformin is negligibly bound to plasma proteins. Metformin partitions into erythrocytes, most likely as a function of time.

Elimination

Metformin has a plasma elimination half-life of approximately 6.2 hours. In blood, the elimination half-life is approximately 17.6 hours, suggesting that the erythrocyte mass may be a compartment of distribution.

Metabolism

Intravenous single-dose studies in normal subjects demonstrate that metformin does not undergo hepatic metabolism (no metabolites have been identified in humans) nor biliary excretion.

Excretion

Following oral administration, approximately 90% of the absorbed drug is excreted via the renal route within the first 24 hours. Renal clearance is approximately 3.5 times greater than creatinine clearance, which indicates that tubular secretion is the major route of metformin elimination.

Specific Populations

Geriatric Patients

SYNJARDY or SYNJARDY XR: Studies characterizing the pharmacokinetics of empagliflozin and metformin after administration of SYNJARDY or SYNJARDY XR in geriatric patients have not been performed [see Warnings and Precautions (5.2) and Use in Specific Populations (8.5)].

Empagliflozin: Age did not have a clinically meaningful impact on the pharmacokinetics of empagliflozin based on a population pharmacokinetic analysis [see Use in Specific Populations (8.5)].

Metformin HCl: Limited data from controlled pharmacokinetic studies of metformin HCl in healthy elderly subjects suggest that total plasma clearance of metformin is decreased, the half-life is prolonged, and Cmax is increased, compared with healthy young subjects. From these data, it appears that the change in metformin pharmacokinetics with aging is primarily accounted for by a change in renal function.

Pediatric Patients

Empagliflozin: The pharmacokinetics and pharmacodynamics of empagliflozin were investigated in pediatric patients aged 10 to 17 years with type 2 diabetes mellitus. Oral administration of empagliflozin at 10 mg and 25 mg resulted in exposure within the range observed in adult patients.

Metformin: After administration of a single oral metformin HCl 500 mg immediate-release tablet with food, geometric mean metformin Cmax and AUC differed less than 5% between pediatric type 2 diabetic patients (12 to 16 years of age) and gender- and weight-matched healthy adults (20 to 45 years of age), all with normal renal function.

Effects of Age, Body Mass Index, Gender, and Race

Empagliflozin: Age, body mass index (BMI), gender and race (Asians versus primarily Whites) do not have a clinically meaningful effect on pharmacokinetics of empagliflozin.

Metformin HCl: No studies of metformin pharmacokinetic parameters according to race have been performed. In controlled clinical studies of metformin HCl in patients with type 2 diabetes mellitus, the antihyperglycemic effect was comparable in Whites (n=249), Blacks or African Americans (n=51), and Hispanics or Latinos (n=24).

Patients with Renal Impairment

SYNJARDY or SYNJARDY XR: Studies characterizing the pharmacokinetics of empagliflozin and metformin HCl after administration of SYNJARDY or SYNJARDY XR in renally impaired patients have not been performed.

Empagliflozin: In adult patients with type 2 diabetes mellitus with mild (eGFR: 60 to less than 90 mL/min/1.73 m^2), moderate (eGFR: 30 to less than 60 mL/min/1.73 m^2), and severe (eGFR: less than 30 mL/min/1.73 m^2) renal impairment and patients on dialysis due to kidney failure, AUC of empagliflozin increased by approximately 18%, 20%, 66%, and 48%, respectively, compared to subjects with normal renal function. Peak plasma levels of empagliflozin were similar in patients with moderate renal impairment and patients on dialysis due to kidney failure, compared to subjects with normal renal function. Peak plasma levels of empagliflozin were roughly 20% higher in patients with mild and severe renal impairment as compared to patients with normal renal function. Population pharmacokinetic analysis showed that the apparent oral clearance of empagliflozin decreased with a decrease in eGFR leading to an increase in drug exposure. However, the fraction of empagliflozin that was excreted unchanged in urine, and urinary glucose excretion, declined with decrease in eGFR.

Metformin HCl: In patients with decreased renal function, the plasma and blood half-life of metformin is prolonged and the renal clearance is decreased [see Contraindications (4) and Warnings and Precautions (5.1)].

Patients with Hepatic Impairment

SYNJARDY or SYNJARDY XR: Studies characterizing the pharmacokinetics of empagliflozin and metformin after administration of SYNJARDY or SYNJARDY XR in hepatically impaired patients have not been performed [see Warnings and Precautions (5.1)].

Empagliflozin: In adult patients with mild, moderate, and severe hepatic impairment according to the Child-Pugh classification, AUC of empagliflozin increased by approximately 23%, 47%, and 75%, and Cmax increased by approximately 4%, 23%, and 48%, respectively, compared to subjects with normal hepatic function.

Metformin HCl: No pharmacokinetic studies of metformin have been conducted in patients with hepatic impairment.

Drug Interaction Studies

Pharmacokinetic drug interaction studies with SYNJARDY or SYNJARDY XR have not been performed; however, such studies have been conducted with the individual components empagliflozin and metformin HCl.

Empagliflozin

In vitro Assessment of Drug Interactions: Empagliflozin does not inhibit, inactivate, or induce CYP450 isoforms. In vitro data suggest that the primary route of metabolism of empagliflozin in humans is glucuronidation by the uridine 5ʹ-diphospho-glucuronosyltransferases UGT1A3, UGT1A8, UGT1A9, and UGT2B7. Empagliflozin does not inhibit UGT1A1, UGT1A3, UGT1A8, UGT1A9, or UGT2B7. Therefore, no effect of empagliflozin is anticipated on concomitantly administered drugs that are substrates of the major CYP450 isoforms or UGT1A1, UGT1A3, UGT1A8, UGT1A9, or UGT2B7. The effect of UGT induction (e.g., induction by rifampicin or any other UGT enzyme inducer) on empagliflozin exposure has not been evaluated.

Empagliflozin is a substrate for P-glycoprotein (P-gp) and breast cancer resistance protein (BCRP), but it does not inhibit these efflux transporters at therapeutic doses. Based on in vitro studies, empagliflozin is considered unlikely to cause interactions with drugs that are P-gp substrates. Empagliflozin is a substrate of the human uptake transporters OAT3, OATP1B1, and OATP1B3, but not OAT1 and OCT2. Empagliflozin does not inhibit any of these human uptake transporters at clinically relevant plasma concentrations and, therefore, no effect of empagliflozin is anticipated on concomitantly administered drugs that are substrates of these uptake transporters.

In vivo Assessment of Drug Interactions: Empagliflozin pharmacokinetics were similar with and without coadministration of metformin HCl, glimepiride, pioglitazone, sitagliptin, linagliptin, warfarin, verapamil, ramipril, and simvastatin in healthy volunteers and with or without coadministration of hydrochlorothiazide and torsemide in patients with type 2 diabetes mellitus (see Figure 1). In subjects with normal renal function, coadministration of empagliflozin with probenecid resulted in a 30% decrease in the fraction of empagliflozin excreted in urine without any effect on 24-hour urinary glucose excretion. The relevance of this observation to patients with renal impairment is unknown.

Figure 1 Effect of Various Medications on the Pharmacokinetics of Empagliflozin as Displayed as 90% Confidence Interval of Geometric Mean AUC and Cmax Ratios [reference lines indicate 100% (80% - 125%)]

aempagliflozin, 50 mg, once daily; bempagliflozin, 25 mg, single dose; cempagliflozin, 25 mg, once daily; dempagliflozin, 10 mg, single dose

Empagliflozin had no clinically relevant effect on the pharmacokinetics of metformin, glimepiride, pioglitazone, sitagliptin, linagliptin, warfarin, digoxin, ramipril, simvastatin, hydrochlorothiazide, torsemide, and oral contraceptives when coadministered in healthy volunteers (see Figure 2).

Figure 2 Effect of Empagliflozin on the Pharmacokinetics of Various Medications as Displayed as 90% Confidence Interval of Geometric Mean AUC and Cmax Ratios [reference lines indicate 100% (80% - 125%)]

aempagliflozin, 50 mg, once daily; bempagliflozin, 25 mg, once daily; cempagliflozin, 25 mg, single dose; dadministered as simvastatin; eadministered as warfarin racemic mixture; fadministered as Microgynon®; gadministered as ramipril

Metformin HCl

Table 5 Effect of Coadministered Drug on Plasma Metformin Systemic Exposure
Coadministered Drug | Dose of Coadministered Drug* | Dose of Metformin HCl* | Geometric Mean Ratio (ratio with/without coadministered drug) No effect=1.0
Coadministered Drug | Dose of Coadministered Drug* | Dose of Metformin HCl* |  | AUC† | Cmax
Glyburide | 5 mg | 500 mg≠ | metformin | 0.98‡ | 0.99‡
Furosemide | 40 mg | 850 mg | metformin | 1.09‡ | 1.22‡
Nifedipine | 10 mg | 850 mg | metformin | 1.16 | 1.21
Propranolol | 40 mg | 850 mg | metformin | 0.90 | 0.94
Ibuprofen | 400 mg | 850 mg | metformin | 1.05‡ | 1.07‡
Cationic drugs eliminated by renal tubular secretion may reduce metformin elimination [see Drug Interactions (7)].
Cimetidine | 400 mg | 850 mg | metformin | 1.40 | 1.61
Carbonic anhydrase inhibitors may cause metabolic acidosis [see Drug Interactions (7)].
Topiramate** | 100 mg | 500 mg | metformin | 1.25 | 1.17
* All metformin and coadministered drugs were given as single doses
† AUC = AUC (INF)
≠ Metformin HCl extended-release tablets 500 mg
‡ Ratio of arithmetic means
**At steady-state with topiramate 100 mg every 12 hours and metformin 500 mg every 12 hours; AUC = AUC (0-12 hours)

Table 6 Effect of Metformin on Coadministered Drug Systemic Exposure
Coadministered Drug | Dose of Coadministered Drug* | Dose of Metformin HCl* | Geometric Mean Ratio (ratio with/without metformin) No effect=1.0
Coadministered Drug | Dose of Coadministered Drug* | Dose of Metformin HCl* |  | AUC† | Cmax
Glyburide | 5 mg | 500 mg§ | glyburide | 0.78‡ | 0.63‡
Furosemide | 40 mg | 850 mg | furosemide | 0.87‡ | 0.69‡
Nifedipine | 10 mg | 850 mg | nifedipine | 1.10§ | 1.08
Propranolol | 40 mg | 850 mg | propranolol | 1.01§ | 0.94
Ibuprofen | 400 mg | 850 mg | ibuprofen | 0.97¶ | 1.01¶
Cimetidine | 400 mg | 850 mg | cimetidine | 0.95§ | 1.01
* All metformin and coadministered drugs were given as single doses
† AUC = AUC (INF) unless otherwise noted
‡ Ratio of arithmetic means, p-value of difference <0.05
§ AUC (0-24 hours) reported
¶ Ratio of arithmetic means

13 NONCLINICAL TOXICOLOGY

13.1 Carcinogenesis, Mutagenesis, Impairment of Fertility

SYNJARDY or SYNJARDY XR

No carcinogenicity, mutagenicity, or impairment of fertility studies have been conducted with the combination of empagliflozin and metformin HCl. General toxicity studies in rats up to 13 weeks were performed with the combined components. These studies indicated that no additive toxicity is caused by the combination of empagliflozin and metformin HCl.

Empagliflozin

Carcinogenesis was evaluated in 2-year studies conducted in CD-1 mice and Wistar rats. Empagliflozin did not increase the incidence of tumors in female rats dosed at 100, 300, or 700 mg/kg/day (up to 72 times the exposure from the maximum clinical dose of 25 mg). In male rats, hemangiomas of the mesenteric lymph node were increased significantly at 700 mg/kg/day or approximately 42 times the exposure from a 25 mg clinical dose. Empagliflozin did not increase the incidence of tumors in female mice dosed at 100, 300, or 1,000 mg/kg/day (up to 62 times the exposure from a 25 mg clinical dose). Renal tubule adenomas and carcinomas were observed in male mice at 1,000 mg/kg/day, which is approximately 45 times the exposure of the maximum clinical dose of 25 mg. These tumors may be associated with a metabolic pathway predominantly present in the male mouse kidney.

Empagliflozin was not mutagenic or clastogenic with or without metabolic activation in the in vitro Ames bacterial mutagenicity assay, the in vitro L5178Y tk+/- mouse lymphoma cell assay, and an in vivo micronucleus assay in rats.

Empagliflozin had no effects on mating, fertility or early embryonic development in treated male or female rats up to the high dose of 700 mg/kg/day (approximately 155 times the 25 mg clinical dose in males and females, respectively).

Metformin HCl

Long-term carcinogenicity studies have been performed in rats (dosing duration of 104 weeks) and mice (dosing duration of 91 weeks) at doses up to and including 900 mg/kg/day and 1,500 mg/kg/day, respectively. These doses are both approximately 4 times the maximum recommended human daily dose of 2,000 mg/kg/day based on body surface area comparisons. No evidence of carcinogenicity with metformin was found in either male or female mice. Similarly, there was no tumorigenic potential observed with metformin in male rats. There was, however, an increased incidence of benign stromal uterine polyps in female rats treated with 900 mg/kg/day.

There was no evidence of a mutagenic potential of metformin in the following in vitro tests: Ames test (Salmonella typhimurium), gene mutation test (mouse lymphoma cells), or chromosomal aberrations test (human lymphocytes). Results in the in vivo mouse micronucleus test were also negative.

Fertility of male or female rats was unaffected by metformin when administered at doses as high as 600 mg/kg/day, which is approximately 2 times the MRHD based on body surface area comparisons.

14 CLINICAL STUDIES

14.1 Glycemic Control Trials in Adults with Type 2 Diabetes Mellitus

In adult patients with type 2 diabetes mellitus, treatment with empagliflozin and metformin HCl produced clinically and statistically significant improvements in HbA1c compared to placebo and metformin HCl. Reductions in HbA1c were observed across subgroups including age, sex, race, and baseline BMI.

Empagliflozin Add-On Combination Therapy with Metformin HCl in Adult Patients with Type 2 Diabetes Mellitus

A total of 637 patients with type 2 diabetes mellitus participated in a double-blind, placebo-controlled trial to evaluate the efficacy of empagliflozin in combination with metformin HCl.

Patients with type 2 diabetes mellitus inadequately controlled on at least 1,500 mg of metformin HCl per day entered an open-label 2-week placebo run-in. At the end of the run-in period, patients who remained inadequately controlled and had an HbA1c between 7% and 10% were randomized to placebo, empagliflozin 10 mg, or empagliflozin 25 mg.

At Week 24, treatment with empagliflozin 10 mg or 25 mg daily provided statistically significant reductions in HbA1c (p-value <0.0001), FPG, and body weight compared with placebo (see Table 7).

Table 7 Results at Week 24 From a Placebo-Controlled Trial for Empagliflozin used in Combination with Metformin HCl
 | Empagliflozin 10 mg N=217 | Empagliflozin 25 mg N=213 | Placebo N=207
HbA1c (%)a
Baseline (mean) | 7.9 | 7.9 | 7.9
Change from baseline (adjusted mean) | -0.7 | -0.8 | -0.1
Difference from placebo + metformin HCl (adjusted mean) (95% CI) | -0.6b (-0.7, -0.4) | -0.6b (-0.8, -0.5) | --
Patients [n (%)] achieving HbA1c <7% | 75 (38%) | 74 (39%) | 23 (13%)
FPG (mg/dL)c
Baseline (mean) | 155 | 149 | 156
Change from baseline (adjusted mean) | -20 | -22 | 6
Difference from placebo + metformin HCl (adjusted mean) | -26 | -29 | --
Body Weight
Baseline mean in kg | 82 | 82 | 80
% change from baseline (adjusted mean) | -2.5 | -2.9 | -0.5
Difference from placebo (adjusted mean) (95% CI) | -2.0b (-2.6, -1.4) | -2.5b (-3.1, -1.9) | --
aModified intent-to-treat population. Last observation on trial (LOCF) was used to impute missing data at Week 24. At Week 24, 9.7%, 14.1%, and 24.6% was imputed for patients randomized to empagliflozin 10 mg, empagliflozin 25 mg, and placebo, respectively.
bANCOVA p-value <0.0001 (HbA1c: ANCOVA model includes baseline HbA1c, treatment, renal function, and region. Body weight and FPG: same model used as for HbA1c but additionally including baseline body weight/baseline FPG, respectively.)
cFPG (mg/dL); for empagliflozin 10 mg, n=216, for empagliflozin 25 mg, n=213, and for placebo, n=207

At Week 24, the systolic blood pressure was statistically significantly reduced compared to placebo by -4.1 mmHg (placebo-corrected, p-value <0.0001) for empagliflozin 10 mg and -4.8 mmHg (placebo-corrected, p-value <0.0001) for empagliflozin 25 mg.

Empagliflozin Initial Combination Therapy with Metformin HCl

A total of 1,364 patients with type 2 diabetes mellitus participated in a double-blind, randomized, active-controlled trial to evaluate the efficacy of empagliflozin in combination with metformin HCl as initial therapy compared to the corresponding individual components.

Treatment-naïve patients with inadequately controlled type 2 diabetes mellitus entered an open-label placebo run-in for 2 weeks. At the end of the run-in period, patients who remained inadequately controlled and had an HbA1c between 7% and 10.5% were randomized to one of 8 active-treatment arms: empagliflozin 10 mg or 25 mg; metformin HCl 1,000 mg, or 2,000 mg; empagliflozin 10 mg in combination with 1,000 mg or 2,000 mg metformin HCl; or empagliflozin 25 mg in combination with 1,000 mg or 2,000 mg metformin HCl.

At Week 24, initial therapy of empagliflozin in combination with metformin HCl provided statistically significant reductions in HbA1c (p-value <0.01) compared to the individual components (see Table 8).

Table 8 Glycemic Parameters at 24 Weeks in a Trial Comparing Empagliflozin and Metformin HCl to the Individual Components as Initial Therapy
 | Empagliflozin 10 mg + Metformin HCl 1,000 mga N=161 | Empagliflozin 10 mg + Metformin HCl 2,000 mga N=167 | Empagliflozin 25 mg + Metformin HCl 1,000 mga N=165 | Empagliflozin 25 mg + Metformin HCl 2,000 mga N=169 | Empagliflozin 10 mg N=169 | Empagliflozin 25 mg N=163 | Metformin HCl 1,000 mga N=167 | Metformin HCl 2,000 mga N=162
HbA1c (%)
Baseline (mean) | 8.7 | 8.7 | 8.8 | 8.7 | 8.6 | 8.9 | 8.7 | 8.6
Change from baseline (adjusted mean) | -2.0 | -2.1 | -1.9 | -2.1 | -1.4 | -1.4 | -1.2 | -1.8
Comparison vs empagliflozin (adjusted mean) (95% CI) | -0.6b (-0.9, -0.4) | -0.7b (-1.0, -0.5) | -0.6c (-0.8, -0.3) | -0.7c (-1.0, -0.5) | -- | -- | -- | --
Comparison vs metformin HCl (adjusted mean) (95% CI) | -0.8b (-1.0, -0.6) | -0.3b (-0.6, -0.1) | -0.8c (-1.0, -0.5) | -0.3c (-0.6, -0.1) | -- | -- | -- | --
Patients [n (%)] achieving HbA1c <7% | 96 (63%) | 112 (70%) | 91 (57%) | 111 (68%) | 69 (43%) | 51 (32%) | 63 (38%) | 92 (58%)
aMetformin HCl total daily dose, administered in two equally divided doses per day.
bp-value ≤0.0062 (modified intent-to-treat population [observed case] MMRM model included treatment, renal function, region, visit, visit by treatment interaction, and baseline HbA1c).
cp-value ≤0.0056 (modified intent-to-treat population [observed case] MMRM model included treatment, renal function, region, visit, visit by treatment interaction, and baseline HbA1c).

Empagliflozin Add-On Combination Therapy with Metformin HCl and Sulfonylurea

A total of 666 patients with type 2 diabetes mellitus participated in a double-blind, placebo-controlled trial to evaluate the efficacy of empagliflozin in combination with metformin HCl plus a sulfonylurea.

Patients with inadequately controlled type 2 diabetes mellitus on at least 1,500 mg per day of metformin HCl and on a sulfonylurea, entered a 2-week open-label placebo run-in. At the end of the run-in, patients who remained inadequately controlled and had an HbA1c between 7% and 10% were randomized to placebo, empagliflozin 10 mg, or empagliflozin 25 mg.

Treatment with empagliflozin 10 mg or 25 mg daily provided statistically significant reductions in HbA1c (p-value <0.0001), FPG, and body weight compared with placebo (see Table 9).

Table 9 Results at Week 24 from a Placebo-Controlled Trial for Empagliflozin in Combination with Metformin HCl and Sulfonylurea
 | Empagliflozin 10 mg N=225 | Empagliflozin 25 mg N=216 | Placebo N=225
HbA1c (%)a
Baseline (mean) | 8.1 | 8.1 | 8.2
Change from baseline (adjusted mean) | -0.8 | -0.8 | -0.2
Difference from placebo (adjusted mean) (95% CI) | -0.6b (-0.8, -0.5) | -0.6b (-0.7, -0.4) | --
Patients [n (%)] achieving HbA1c <7% | 55 (26%) | 65 (32%) | 20 (9%)
FPG (mg/dL)c
Baseline (mean) | 151 | 156 | 152
Change from baseline (adjusted mean) | -23 | -23 | 6
Difference from placebo (adjusted mean) | -29 | -29 | --
Body Weight
Baseline mean in kg | 77 | 78 | 76
% change from baseline (adjusted mean) | -2.9 | -3.2 | -0.5
Difference from placebo (adjusted mean) (95% CI) | -2.4b (-3.0, -1.8) | -2.7b (-3.3, -2.1) | --
aModified intent-to-treat population. Last observation on trial (LOCF) was used to impute missing data at Week 24. At Week 24, 17.8%, 16.7%, and 25.3% was imputed for patients randomized to empagliflozin 10 mg, empagliflozin 25 mg, and placebo, respectively.
bANCOVA p-value <0.0001 (HbA1c: ANCOVA model includes baseline HbA1c, treatment, renal function, and region. Body weight and FPG: same model used as for HbA1c but additionally including baseline body weight/baseline FPG, respectively.)
cFPG (mg/dL); for empagliflozin 10 mg, n=225, for empagliflozin 25 mg, n=215, for placebo, n=224

Active-Controlled Trial vs Glimepiride in Combination with Metformin HCl

The efficacy of empagliflozin was evaluated in a double-blind, glimepiride-controlled, trial in 1,545 patients with type 2 diabetes mellitus with insufficient glycemic control despite metformin HCl therapy.

Patients with inadequate glycemic control and an HbA1c between 7% and 10% after a 2-week run-in period were randomized to glimepiride or empagliflozin 25 mg.

At Week 52, empagliflozin 25 mg and glimepiride lowered HbA1c and FPG (see Table 10, Figure 3). The difference in observed effect size between empagliflozin 25 mg and glimepiride excluded the pre-specified non-inferiority margin of 0.3%. The mean daily dosage of glimepiride was 2.7 mg and the maximal approved dosage in the United States is 8 mg per day.

Table 10 Results at Week 52 from an Active-Controlled Trial Comparing Empagliflozin to Glimepiride as Add-On Therapy in Patients Inadequately Controlled on Metformin HCl
 | Empagliflozin 25 mg N=765 | Glimepiride N=780
HbA1c (%)a
Baseline (mean) | 7.9 | 7.9
Change from baseline (adjusted mean) | -0.7 | -0.7
Difference from glimepiride (adjusted mean) (97.5% CI) | -0.07b (-0.15, 0.01) | --
FPG (mg/dL)d
Baseline (mean) | 150 | 150
Change from baseline (adjusted mean) | -19 | -9
Difference from glimepiride (adjusted mean) | -11 | --
Body Weight
Baseline mean in kg | 82.5 | 83
% change from baseline (adjusted mean) | -3.9 | 2.0
Difference from glimepiride (adjusted mean) (95% CI) | -5.9c (-6.3, -5.5) | --
aModified intent-to-treat population. Last observation on trial (LOCF) was used to impute data missing at Week 52. At Week 52, data was imputed for 15.3% and 21.9% of patients randomized to empagliflozin 25 mg and glimepiride, respectively.
bNon-inferior, ANCOVA model p-value <0.0001 (HbA1c: ANCOVA model includes baseline HbA1c, treatment, renal function, and region)
cANCOVA p-value <0.0001 (Body weight and FPG: same model used as for HbA1c but additionally including baseline body weight/baseline FPG, respectively.)
dFPG (mg/dL); for empagliflozin 25 mg, n=764, for glimepiride, n=779

Figure 3 Adjusted mean HbA1c Change at Each Time Point (Completers) and at Week 52 (mITT Population) – LOCF

At Week 52, the adjusted mean change from baseline in systolic blood pressure was -3.6 mmHg, compared to 2.2 mmHg for glimepiride. The differences between treatment groups for systolic blood pressure was statistically significant (p-value <0.0001).

At Week 104, the adjusted mean change from baseline in HbA1c was -0.75% for empagliflozin 25 mg and -0.66% for glimepiride. The adjusted mean treatment difference was -0.09% with a 97.5% confidence interval of (-0.32%, 0.15%), excluding the pre-specified non-inferiority margin of 0.3%. The mean daily dosage of glimepiride was 2.7 mg and the maximal approved dosage in the United States is 8 mg per day. The Week 104 analysis included data with and without concomitant glycemic rescue medication, as well as off-treatment data. Missing data for patients not providing any information at the visit were imputed based on the observed off-treatment data. In this multiple imputation analysis, 13.9% of the data were imputed for empagliflozin 25 mg and 12.9% for glimepiride.

At Week 104, empagliflozin 25 mg daily resulted in a statistically significant difference in change from baseline for body weight compared to glimepiride (-3.1 kg for empagliflozin 25 mg vs. +1.3 kg for glimepiride; ANCOVA-LOCF, p-value <0.0001).

14.2 Glycemic Control Trials in Pediatric Patients with Type 2 Diabetes Mellitus

Glycemic Control Trial of Empagliflozin in Pediatric Patients Aged 10 to 17 Years with Type 2 Diabetes Mellitus

DINAMO (NCT03429543) was a 26-week, double-blind, randomized, placebo-controlled, parallel group trial, with a double-blind active treatment safety extension period up to 52 weeks to assess the efficacy of empagliflozin. The trial enrolled pediatric patients aged 10 to 17 years with inadequately controlled type 2 diabetes mellitus (HbA1c 6.5 to 10.5%). Patients treated with metformin HCl (at least 1,000 mg daily or maximally tolerated dose), with or without insulin therapy, and those with a history of intolerance to metformin HCl therapy were enrolled. Patients were randomized to 3 treatment arms (empagliflozin 10 mg, a dipeptidyl peptidase-4 (DPP-4) inhibitor, or placebo) over 26 weeks. Patients in the empagliflozin 10 mg group who failed to achieve HbA1c <7.0% at Week 12 underwent a second randomization at Week 14 to remain on the 10 mg dose or increase to 25 mg. Patients on placebo were re-randomized at Week 26 to one of the empagliflozin doses (10 mg or 25 mg) or a DPP-4 inhibitor.

A total of 157 patients were treated with either empagliflozin (10 mg or 25 mg; N=52), a DPP-4 inhibitor (N=52), or placebo (N=53). Background therapies as adjunct to diet and exercise included metformin HCl (51%), a combination of metformin HCl and insulin (40.1%), insulin (3.2%), or none (5.7%). The mean HbA1c at baseline was 8.0% and the mean duration of type 2 diabetes mellitus was 2.1 years. The mean age was 14.5 years (range: 10-17 years) and 51.6% were aged 15 years and older. Approximately, 50% were White, 6% were Asian, 31% were Black or African American, and 38% were of Hispanic or Latino ethnicity. The mean BMI was 36.0 kg/m^2 and mean BMI Z-score was 3.0. Patients with an eGFR less than 60 mL/min/1.73 m^2 were not enrolled in the trial. Approximately 25% of the trial population had microalbuminuria or macroalbuminuria.

At Week 26, treatment with empagliflozin was superior in reducing HbA1c from baseline versus placebo (see Table 11).

Table 11 Results at Week 26 for a Placebo-Controlled Trial for Empagliflozin in Combination with Metformin HCl and/or Insulin or as Monotherapy in Pediatric Patients Aged 10 to 17 Years with Type 2 Diabetes Mellitusa
 | Empagliflozin 10 mg and 25 mg | Placebo
HbA1c (%)b
Number of patients | n=52 | n=53
Baseline (mean) | 8.0 | 8.1
Change from baselinec | -0.2 | 0.7
Difference from placeboc (95% CI) | -0.8e (-1.5, -0.2) | --
FPG (mg/dL)b,d
Number of patients | n=48 | n=52
Baseline (mean) | 154 | 159
Change from baselinec | -19 | 17
Difference from placeboc (95% CI) | -36 (-60.7, -10.7) | --
aModified intent-to-treat set (All randomized and treated patients with baseline measurement).
bMultiple imputations using placebo wash-out approach with 500 iterations for missing data. Imputed for HbA1c (empagliflozin N=5 (9.6%), placebo N=3 (5.7%)), for FPG (empagliflozin N=4 (8.3%), placebo N=2 (3.8%)).
cLeast-Square Mean from Analysis of Covariance (ANCOVA) adjusted for baseline value and baseline age stratum (< 15 years vs 15 to < 18 years).
dNot evaluated for statistical significance, not part of sequential testing procedure.
ep-value=0.0116 (two-sided)

Glycemic Control Trial of Metformin HCl Immediate-Release in Pediatric Patients Aged 10 to 16 Years with Type 2 Diabetes Mellitus:

A double-blind, placebo-controlled trial was conducted in pediatric patients aged 10 to 16 years with type 2 diabetes mellitus (mean FPG 182.2 mg/dL), where patients were treated with metformin HCl immediate-release tablets (up to 2,000 mg/day) for up to 16 weeks (mean duration of treatment 11 weeks). The results are displayed in Table 12.

Table 12 Mean Change in Fasting Plasma Glucose at Week 16 Comparing Metformin HCl vs. Placebo in Pediatric Patientsa with Type 2 Diabetes Mellitus
 | Metformin HCl | Placebo | p-value
FPG (mg/dL) | (n=37) | (n=36)
Baseline | 162.4 | 192.3
Change at FINAL VISIT | -42.9 | 21.4 | <0.001
a Pediatric patients mean age 13.8 years (range 10-16 years)

Mean baseline body weight was 205 lbs and 189 lbs in the metformin HCl immediate-release and placebo arms, respectively. Mean change in body weight from baseline to week 16 was -3.3 lbs and -2.0 lbs in the metformin HCl and placebo arms, respectively.

14.3 Empagliflozin CV Outcome Trial in Adult Patients with Type 2 Diabetes Mellitus and Atherosclerotic CV Disease

EMPA-REG OUTCOME was a multicenter, multinational, randomized, double-blind parallel group trial that compared the risk of experiencing a major adverse CV event (MACE) between empagliflozin and placebo when these were added to and used concomitantly with standard of care treatments for diabetes mellitus and atherosclerotic CV disease. Concomitant antidiabetic medications were kept stable for the first 12 weeks of the trial. Thereafter, antidiabetic and atherosclerotic therapies could be adjusted, at the discretion of investigators, to ensure participants were treated according to the standard care for these diseases.

A total of 7,020 patients were treated (empagliflozin 10 mg = 2,345; empagliflozin 25 mg = 2,342; placebo = 2,333) and followed for a median of 3.1 years. Approximately 72% of the trial population was White, 22% was Asian, and 5% was Black or African American. The mean age was 63 years and approximately 72% were male.

All patients in the trial had inadequately controlled type 2 diabetes mellitus at baseline (HbA1c greater than or equal to 7%). The mean HbA1c at baseline was 8.1% and 57% of participants had diabetes mellitus for more than 10 years. Approximately 31%, 22% and 20% reported a past history of neuropathy, retinopathy and nephropathy to investigators, respectively and the mean eGFR was 74 mL/min/1.73 m^2. At baseline, patients were treated with one (~30%) or more (~70%) antidiabetic medications including metformin HCl (74%), insulin (48%), and sulfonylurea (43%).

All patients had established atherosclerotic CV disease at baseline including one (82%) or more (18%) of the following: a documented history of coronary artery disease (76%), stroke (23%) or peripheral artery disease (21%). At baseline, the mean systolic blood pressure was 136 mmHg, the mean diastolic blood pressure was 76 mmHg, the mean LDL was 86 mg/dL, the mean HDL was 44 mg/dL, and the mean urinary albumin to creatinine ratio (UACR) was 175 mg/g. At baseline, approximately 81% of patients were treated with renin angiotensin system inhibitors, 65% with beta-blockers, 43% with diuretics, 77% with statins, and 86% with antiplatelet agents (mostly aspirin).

The primary endpoint in EMPA-REG OUTCOME was the time to first occurrence of a Major Adverse Cardiac Event (MACE). A major adverse cardiac event was defined as occurrence of either a CV death or a non-fatal myocardial infarction (MI) or a non-fatal stroke. The statistical analysis plan had pre-specified that the 10 and 25 mg dosages would be combined. A Cox proportional hazards model was used to test for non-inferiority against the pre-specified risk margin of 1.3 for the hazard ratio of MACE and superiority on MACE if non-inferiority was demonstrated. Type-1 error was controlled across multiples tests using a hierarchical testing strategy.

Empagliflozin significantly reduced the risk of first occurrence of primary composite endpoint of CV death, non-fatal myocardial infarction, or non-fatal stroke (HR: 0.86; 95% CI: 0.74, 0.99). The treatment effect was due to a significant reduction in the risk of CV death in subjects randomized to empagliflozin (HR: 0.62; 95% CI: 0.49, 0.77), with no change in the risk of non-fatal myocardial infarction or non-fatal stroke (see Table 13 and Figures 4 and 5). Results for the 10 mg and 25 mg empagliflozin dosages were consistent with results for the combined dosage groups.

Table 13 Treatment Effect for the Primary Composite Endpoint and its Componentsa
 | Placebo N=2,333 | Empagliflozin N=4,687 | Hazard ratio vs placebo (95% CI)
Composite of CV death, non-fatal myocardial infarction, non-fatal stroke (time to first occurrence)b | 282 (12.1%) | 490 (10.5%) | 0.86 (0.74, 0.99)
Non-fatal myocardial infarctionc | 121 (5.2%) | 213 (4.5%) | 0.87 (0.70, 1.09)
Non-fatal strokec | 60 (2.6%) | 150 (3.2%) | 1.24 (0.92, 1.67)
CV deathc | 137 (5.9%) | 172 (3.7%) | 0.62 (0.49, 0.77)
aTreated set (patients who had received at least one dose of trial drug)
bp-value for superiority (2-sided) 0.04
cTotal number of events

Figure 4 Estimated Cumulative Incidence of First MACE

Figure 5 Estimated Cumulative Incidence of CV Death

The efficacy of empagliflozin on CV death was generally consistent across major demographic and disease subgroups.

Vital status was obtained for 99.2% of subjects in the trial. A total of 463 deaths were recorded during the EMPA-REG OUTCOME trial. Most of these deaths were categorized as CV deaths. The non-CV deaths were only a small proportion of deaths and were balanced between the treatment groups (2.1% in patients treated with empagliflozin, and 2.4% of patients treated with placebo).

14.4 Empagliflozin Heart Failure Trials, Including Adult Patients with Type 2 Diabetes Mellitus

EMPEROR-Reduced Trial (Chronic Heart Failure with Left Ventricular Ejection Fraction ≤ 40%)

EMPEROR-Reduced (NCT03057977) was a double-blind trial conducted in adults with chronic heart failure [New York Heart Association (NYHA) functional class II-IV] with left ventricular ejection fraction (LVEF) ≤40% to evaluate the efficacy of empagliflozin as adjunct to standard of care heart failure therapy. Of 3,730 patients, 1,863 were randomized to empagliflozin 10 mg once daily and 1,867 to placebo once daily and were followed for a median of 16 months.

Baseline Disease Characteristics and Demographics

EMPEROR-Reduced included patients with type 2 diabetes mellitus (n=1,856) and patients without type 2 diabetes mellitus (n=1,874). The mean age of the trial population was 67 years (range: 25 to 94 years) and 76% were males, 24% were women, and 27% were 75 years of age or older. Approximately 71% of the trial population were White, 18% Asian and 7% Black or African American. At randomization, 75% of patients were NYHA class II, 24% were class III and 0.5% were class IV. The mean LVEF was 28%. At baseline, the mean eGFR was 62 mL/min/1.73 m^2 and the median urinary albumin to creatinine ratio (UACR) was 22 mg/g. Approximately half of the patients (52%) had eGFR equal to or above 60 mL/min/1.73 m^2, 24% had eGFR 45 to less than 60 mL/min/1.73 m^2, and 19% had eGFR 30 to less than 45 mL/min/1.73 m^2. At baseline, 88% of patients were treated with angiotensin-converting enzyme (ACE) inhibitors, angiotensin receptor blockers (ARB), or angiotensin receptor-neprilysin inhibitors (ARNI), 95% with beta-blockers, 71% with mineralocorticoid receptor antagonists (MRA), and 95% with diuretics.

In EMPEROR-Reduced, history of type 2 diabetes mellitus was present in 50% of the patients, and 46% of these patients were treated with metformin HCl (444 patients in the empagliflozin group and 418 in the placebo group) and 25% were treated with insulin. In the type 2 diabetes mellitus subpopulation, the mean age was 67 years; 77% were males; 69% White, 19% Asian and 7% Black or African American; 32% were Hispanic/Latino. In the type 2 diabetes mellitus subpopulation, at baseline, 71% of patients were classified as NYHA class II, 28% class III and 0.7% class IV; the mean LVEF was 27%; the mean baseline eGFR was 61 mL/min/1.73 m^2. In this subpopulation, at baseline, 88% of patients were treated with ACE inhibitors, ARB, or ARNI, 95% with beta-blockers, 70% with MRA, and 96% with diuretics.

Results

In EMPEROR-Reduced, empagliflozin 10 mg, compared with placebo, reduced the risk of the primary composite endpoint of CV death or hospitalization for heart failure (HHF) mostly through a reduction in HHF (HR 0.75 [95% CI 0.65, 0.86]). Empagliflozin reduced the risk of first and recurrent HHF, a key secondary endpoint. Because of the metformin HCl component, SYNJARDY and SYNJARDY XR are not indicated for use in patients with heart failure without type 2 diabetes mellitus [see Indications and Usage (1)].

The effect of empagliflozin in reducing the risk of the primary composite endpoint was consistent in patients with type 2 diabetes mellitus (HR 0.73 [95% CI 0.60, 0.87]), and in patients with type 2 diabetes mellitus and metformin HCl as background therapy (HR 0.65 [95% CI 0.49, 0.86]).

EMPEROR-Preserved Trial (Chronic Heart Failure with Left Ventricular Ejection Fraction > 40%)

EMPEROR-Preserved (NCT03057951) was a double-blind trial conducted in patients with chronic heart failure NYHA Class II-IV with LVEF >40% to evaluate the efficacy of empagliflozin as adjunct to standard of care therapy. Of 5,988 patients, 2,997 patients were randomized to empagliflozin 10 mg once daily and 2,991 patients to placebo once daily and were followed for a median of 26 months.

Baseline Disease Characteristics and Demographics

EMPEROR-Preserved included patients with type 2 diabetes mellitus (n=2,928) and patients without type 2 diabetes mellitus (n=3,060). The mean age of the trial population was 72 years (range: 22 to 100 years) and 55% were males, 45% were women, and 43% were 75 years of age or older. Approximately 76% of the trial population were White, 14% Asian and 4% Black or African American. At randomization, 82% of patients were NYHA class II, 18% were class III and 0.3% were class IV. This trial included patients with a LVEF <50% (33.1%), with a LVEF 50 to <60% (34.4%) and a LVEF ≥60% (32.5%). At baseline, the mean eGFR was 61 mL/min/1.73 m^2 and the median urinary albumin to creatinine ratio (UACR) was 21 mg/g. Approximately half of the patients (50%) had eGFR equal to or above 60 mL/min/1.73 m^2, 26% had eGFR 45 to less than 60 mL/min/1.73 m^2, and 19% had eGFR 30 to less than 45 mL/min/1.73 m^2. At baseline, 81% of patients were treated with ACE inhibitors, ARBs, or ARNI, 86% with beta-blockers, 38% with MRAs, and 86% with diuretics.

In EMPEROR-Preserved, history of type 2 diabetes mellitus was present in 49% of the patients, and 54% of these patients were treated with metformin HCl (773 patients in the empagliflozin group and 803 in the placebo group) and 29% were treated with insulin. In the type 2 diabetes mellitus subpopulation, the mean age was 71 years, 57% were males, 75% White, 13% Asian and 5% Black or African American. In the type 2 diabetes mellitus subpopulation, at baseline, 79% of patients were classified as NYHA class II, 20% class III and 0.2% class IV; the trial also included type 2 diabetics with LVEF <50% (35%), with a LVEF 50 to <60% (34%) and a LVEF ≥60% (31%). For this subpopulation, the mean baseline eGFR was 60 mL/min/1.73 m^2; and at baseline, 83% of patients were treated with ACE inhibitors, ARB, or ARNI, 88% with beta-blockers, 39% with MRA, and 89% with diuretics.

Results

In EMPEROR-Preserved, empagliflozin 10 mg, compared with placebo, reduced the risk of the primary composite endpoint (time to first event of either CV death or HHF) mostly through a reduction in hospitalization for heart failure (HR 0.79 [95% CI 0.69, 0.90]). Empagliflozin reduced the risk of first and recurrent HHF, a key secondary endpoint. Because of the metformin HCl component, SYNJARDY and SYNJARDY XR are not indicated for use in patients with heart failure without type 2 diabetes mellitus [see Indications and Usage (1)].

The effect of empagliflozin in reducing the risk of the primary composite endpoint was consistent in patients with type 2 diabetes mellitus (HR 0.80 [95% CI 0.67, 0.95]), and in patients with type 2 diabetes mellitus and metformin HCl as background therapy (HR 0.79 [95% CI 0.61, 1.02]).

14.5 Empagliflozin Chronic Kidney Disease Trial, Including Adult Patients with Type 2 Diabetes Mellitus

The effectiveness of empagliflozin, a component of SYNJARDY and SYNJARDY XR, to reduce the risk of sustained decline in eGFR, end-stage kidney disease, CV death, and hospitalization has been established in adults with chronic kidney disease at risk of progression based on an adequate and well-controlled study of empagliflozin [EMPA-KIDNEY (NCT03594110)]. This trial was designed to determine the treatment effect of empagliflozin compared to placebo in adults with CKD (with and without type 2 diabetes). The trial, which studied empagliflozin rather than SYNJARDY or SYNJARDY XR, included adults taking metformin HCl as a concomitant medication. The efficacy results of EMPA-KIDNEY are reported below.

EMPA-KIDNEY was a randomized, double-blind, placebo-controlled trial conducted in adults with chronic kidney disease [eGFR ≥20 to <45 mL/min/1.73 m^2; or eGFR ≥45 to <90 mL/min/1.73 m^2 with urine albumin to creatinine ratio (UACR) ≥200 mg/g]. The trial excluded patients with polycystic kidney disease or patients requiring intravenous immunosuppressive therapy in the preceding three months or >45 mg of prednisone (or equivalent) at the time of screening. The primary objective of the trial was to assess the effects of empagliflozin as an adjunct to standard of care therapy, including RAS-inhibitor therapy when appropriate, on time to kidney disease progression or CV death. A total of 6,609 patients, were equally randomized to empagliflozin 10 mg orally once-daily or placebo and were followed for a median of 24 months.

Baseline Disease Characteristics and Demographics

EMPA-KIDNEY included patients with type 2 diabetes mellitus (n=2,936) and patients without type 2 diabetes mellitus (n=3,673). The mean age of the study population was 63 years (range: 18 to 94 years) and 67% were male. Approximately 58% of the study population were White, 36% Asian, and 4% Black or African American. At baseline, the mean eGFR was 37 mL/min/1.73 m^2, 21% of patients had an eGFR equal to or above 45 mL/min/1.73 m^2, and 44% had an eGFR 30 to less than 45 mL/min/1.73 m^2. The median UACR was 329 mg/g, 20% of patients had a UACR <30 mg/g, 28% had a UACR 30 to ≤300 mg/g, and 52% had a UACR >300 mg/g. The most common etiologies of CKD were diabetic nephropathy/diabetic kidney disease (31%), glomerular disease (25%), hypertensive/renovascular disease (22%) and other/unknown (22%). At baseline, 85% of patients were treated with angiotensin-converting enzyme (ACE) inhibitor or angiotensin receptor blocker (ARB), 64% with statins, and 34% with antiplatelet agents.

In EMPA-KIDNEY, history of type 2 diabetes mellitus was present in 44% of the patients, and 23% of these patients were treated with metformin HCl (329 patients in the empagliflozin group and 334 in the placebo group). In the type 2 diabetes mellitus subpopulation, the mean age was 68 years, 67% were males, 59% White, 33% Asian and 6% Black or African American. In the type 2 diabetes mellitus subpopulation, at baseline, the mean eGFR was 36 mL/min/1.73 m^2, 17% of patients had an eGFR equal to or above 45 mL/min/1.73 m^2, and 45% had an eGFR 30 to less than 45 mL/min/1.73 m^2; the median UACR was 256 mg/g, 22% of patients had a UACR <30 mg/g, 31% had a UACR 30 to ≤300 mg/g, and 47% had a UACR >300 mg/g. The most common etiologies of CKD at baseline in this subpopulation were diabetic nephropathy/diabetic kidney disease (67%), glomerular disease (6%), hypertensive/renovascular disease (14%) and other/unknown (13%). In this subpopulation, at baseline, 85% of patients were treated with ACE inhibitor or ARB, 79% with statins, and 48% with antiplatelet agents.

Results

In EMPA-KIDNEY, empagliflozin 10 mg, compared with placebo, reduced the risk of the primary composite endpoint of sustained ≥40% eGFR decline, sustained eGFR <10 mL/min/1.73 m^2, progression to end-stage kidney disease, or CV or renal death. The treatment effect reflected a reduction in a sustained ≥40% eGFR decline, sustained eGFR <10 mL/min/1.73 m^2, progression to end-stage kidney disease, and CV death. There were few renal deaths during the trial. Empagliflozin also reduced the risk of first and recurrent hospitalization; information collected on the reason for hospitalization was insufficient to further characterize the benefit. Because of the metformin HCl component, SYNJARDY and SYNJARDY XR are not indicated for use in patients with CKD without type 2 diabetes mellitus [see Indications and Usage (1)].

The effect of empagliflozin in reducing the risk of the primary composite endpoint was consistent in patients with type 2 diabetes mellitus [HR 0.65 (95% CI 0.54, 0.78)], and in patients with type 2 diabetes mellitus and metformin HCl as background therapy [HR 0.72 (95% CI 0.48, 1.09)].

16 HOW SUPPLIED/STORAGE AND HANDLING

SYNJARDY tablets are available as follows:

Tablet Strength | Color/Shape | Tablet Markings | Package Size | NDC Number
5 mg Empagliflozin 500 mg Metformin HCl | orange yellow, oval, biconvex, film-coated tablet | Boehringer Ingelheim company symbol and "S5" debossed on one side; the other side is debossed with "500". | Bottles of 60 Bottles of 180 | 0597-0159-60 0597-0159-18
5 mg Empagliflozin 1,000 mg Metformin HCl | brownish yellow, oval, biconvex, film-coated tablet | Boehringer Ingelheim company symbol and "S5" debossed on one side; the other side is debossed with "1000". | Bottles of 60 Bottles of 180 | 0597-0175-60 0597-0175-18
12.5 mg Empagliflozin 500 mg Metformin HCl | pale brownish purple, oval, biconvex, film-coated tablet | Boehringer Ingelheim company symbol and "S12" debossed on one side; the other side is debossed with "500". | Bottles of 60 Bottles of 180 | 0597-0180-60 0597-0180-18
12.5 mg Empagliflozin 1,000 mg Metformin HCl | dark brownish purple, oval, biconvex, film-coated tablet | Boehringer Ingelheim company symbol and "S12" debossed on one side; the other side is debossed with "1000". | Bottles of 60 Bottles of 180 | 0597-0168-60 0597-0168-18

SYNJARDY XR extended-release tablets are available as follows:

Tablet Strength | Color/Shape | Tablet Markings | Package Size | NDC Number
5 mg Empagliflozin 1,000 mg Metformin HCl | olive green, oval, biconvex, film-coated tablet | Printed on one side in black ink with the Boehringer Ingelheim company symbol and "S5" on the top line and "1000 M" on the bottom line. | Bottles of 60 Bottles of 180 | 0597-0290-74 0597-0290-59
10 mg Empagliflozin 1,000 mg Metformin HCl | orange, oval, biconvex, film-coated tablet | Printed on one side in black ink with the Boehringer Ingelheim company symbol and "S10" on the top line and "1000 M" on the bottom line. | Bottles of 30 Bottles of 90 | 0597-0280-73 0597-0280-90
12.5 mg Empagliflozin 1,000 mg Metformin HCl | blue, oval, biconvex, film-coated tablet | Printed on one side in black ink with the Boehringer Ingelheim company symbol and "S12" on the top line and "1000 M" on the bottom line. | Bottles of 60 Bottles of 180 | 0597-0300-45 0597-0300-93
25 mg Empagliflozin 1,000 mg Metformin HCl | light green, oval, biconvex, film-coated tablet | Printed on one side in black ink with the Boehringer Ingelheim company symbol and "S25" on the top line and "1000 M" on the bottom line. | Bottles of 30 Bottles of 90 | 0597-0295-88 0597-0295-78

Storage

Store at 20°C to 25°C (68°F to 77°F); excursions permitted to 15°C to 30°C (59°F to 86°F) [see USP Controlled Room Temperature].

17 PATIENT COUNSELING INFORMATION

Advise the patient to read the FDA-approved patient labeling (Medication Guide).

Lactic Acidosis

Inform patients of the risks of lactic acidosis due to metformin, its symptoms, and conditions that predispose to its development. Advise patients to discontinue SYNJARDY or SYNJARDY XR immediately and to notify their healthcare provider promptly if unexplained hyperventilation, malaise, myalgia, unusual somnolence, or other nonspecific symptoms occur. Counsel patients against excessive alcohol intake and inform patients about the importance of regular testing of renal function while receiving SYNJARDY or SYNJARDY XR. Instruct patients to inform their healthcare provider that they are taking SYNJARDY or SYNJARDY XR prior to any surgical or radiological procedure, as temporary discontinuation may be required until renal function has been confirmed to be normal [see Warnings and Precautions (5.1)].

Diabetic Ketoacidosis in Patients with Type 1 Diabetes Mellitus and Other Ketoacidosis

Inform patients that SYNJARDY or SYNJARDY XR can cause potentially fatal ketoacidosis and that type 2 diabetes mellitus and pancreatic disorders (e.g., history of pancreatitis or pancreatic surgery) are risk factors.

Educate all patients on precipitating factors (such as insulin dose reduction or missed insulin doses, infection, reduced caloric intake, ketogenic diet, surgery, dehydration, and alcohol abuse) and symptoms of ketoacidosis (including nausea, vomiting, abdominal pain, tiredness, and labored breathing). Inform patients that blood glucose may be normal even in the presence of ketoacidosis.

Advise patients that they may be asked to monitor ketones. If symptoms of ketoacidosis occur, instruct patients to discontinue SYNJARDY or SYNJARDY XR and seek medical attention immediately [see Warnings and Precautions (5.2)].

Volume Depletion

Inform patients that symptomatic hypotension may occur with SYNJARDY or SYNJARDY XR and advise them to contact their healthcare provider if they experience such symptoms [see Warnings and Precautions (5.3)]. Inform patients that dehydration may increase the risk for hypotension, and to maintain adequate fluid intake.

Genitourinary Infections, including Urosepsis, Pyelonephritis, Necrotizing Fasciitis of the Perineum (Fournier's Gangrene), and Genital Mycotic Infections

Counsel patients that genitourinary infections may occur when taking empagliflozin, a component of SYNJARDY and SYNJARDY XR, and may become serious. Educate them on the symptoms and advise them to seek medical advice if symptoms occur. Specifically, advise patients to promptly seek medical attention if they develop pain or tenderness, redness, or swelling of the genitals or the area from the genitals back to the rectum, along with a fever above 100.4°F or malaise [see Warnings and Precautions (5.4)].

Hypoglycemia

Inform patients that hypoglycemia has been reported when SYNJARDY or SYNJARDY XR is used with insulin secretagogues or insulin. Hypoglycemia may occur in pediatric patients regardless of concomitant antidiabetic treatment. Educate patients or caregivers on the signs and symptoms of hypoglycemia [see Warnings and Precautions (5.5)].

Lower Limb Amputation

Counsel patients about the importance of routine preventative foot care. Instruct patients to monitor for new pain or tenderness, sores or ulcers, or infections involving the leg or foot and to seek medical advice immediately if such signs or symptoms develop [see Warnings and Precautions (5.6)].

Hypersensitivity Reactions

Inform patients that serious hypersensitivity reactions, such as urticaria and angioedema, have been reported with empagliflozin, a component of SYNJARDY and SYNJARDY XR. Advise patients to report immediately any skin reaction or angioedema, and to discontinue the drug until they have consulted prescribing healthcare provider [see Warnings and Precautions (5.7)].

Vitamin B12 Deficiency

Inform patients about the importance of regular hematological parameters while receiving SYNJARDY or SYNJARDY XR [see Warnings and Precautions (5.8)].

Laboratory Tests

Inform patients that elevated glucose in urinalysis is expected when taking SYNJARDY or SYNJARDY XR [see Drug Interactions (7)].

Pregnancy

Advise pregnant patients, and patients of reproductive potential, of the potential risk to a fetus with treatment with SYNJARDY or SYNJARDY XR [see Use in Specific Populations (8.1)]. Instruct patients to report pregnancies to their healthcare provider as soon as possible.

Lactation

Advise patients that breastfeeding is not recommended during treatment with SYNJARDY or SYNJARDY XR [see Use in Specific Populations (8.2)].

Patients of Reproductive Potential

Inform patients that treatment with metformin HCl may result in ovulation in some premenopausal anovulatory patients, which may lead to unintended pregnancy [see Use in Specific Populations (8.3)].

Administration Instructions

Inform patients that SYNJARDY XR tablets must be swallowed whole and never split, crushed, dissolved, or chewed and that incompletely dissolved SYNJARDY XR tablets may be eliminated in the feces.

Missed Dose

Instruct patients to take SYNJARDY or SYNJARDY XR only as prescribed. If a dose is missed, it should be taken as soon as the patient remembers. Advise patients not to double their next dose [see Dosage and Administration (2.7)].

Distributed by:
Boehringer Ingelheim Pharmaceuticals, Inc.
Ridgefield, CT 06877 USA

Licensed from:
Boehringer Ingelheim International GmbH, Ingelheim, Germany

SYNJARDY is a registered trademark of and used under license from Boehringer Ingelheim International GmbH.

Boehringer Ingelheim Pharmaceuticals, Inc. either owns or uses the Jardiance®, EMPA-REG OUTCOME®, EMPEROR-Reduced®, EMPEROR-Preserved®, and EMPA-KIDNEY® trademarks under license.

The other brands listed are trademarks of their respective owners and are not trademarks of Boehringer Ingelheim Pharmaceuticals, Inc.

Copyright © 2026 Boehringer Ingelheim International GmbH
ALL RIGHTS RESERVED

COL12574FA072026

SPL8978L

MEDICATION GUIDE
SYNJARDY® (sin-JAR-dee)
(empagliflozin and metformin hydrochloride tablets), for oral use
and
SYNJARDY® XR (sin-JAR-dee XR)
(empagliflozin and metformin hydrochloride extended-release tablets), for oral use

What is the most important information I should know about SYNJARDY or SYNJARDY XR?
SYNJARDY or SYNJARDY XR can cause serious side effects, including:

- Lactic Acidosis. Metformin hydrochloride (HCl), one of the medicines in SYNJARDY and SYNJARDY XR, can cause a rare but serious condition called lactic acidosis (a build-up of lactic acid in the blood) that can cause death. Lactic acidosis is a medical emergency and must be treated in a hospital.
  Stop taking SYNJARDY or SYNJARDY XR and call your healthcare provider right away or go to the nearest hospital emergency room if you get any of the following symptoms of lactic acidosis:

- feel very weak and tired
- have unusual (not normal) muscle pain
- have trouble breathing
- have unexplained stomach or intestinal problems with nausea and vomiting, or diarrhea

- have unusual sleepiness or sleep longer than usual
- feel cold, especially in your arms and legs
- feel dizzy or lightheaded
- have a slow or irregular heartbeat

You have a higher chance of getting lactic acidosis with SYNJARDY or SYNJARDY XR if you:

- have moderate to severe kidney problems.
- have liver problems.
- drink a lot of alcohol (very often or short-term "binge" drinking).
- get dehydrated (lose a large amount of body fluids). This can happen if you are sick with a fever, vomiting, or diarrhea. Dehydration can also happen when you sweat a lot with activity or exercise and do not drink enough fluids.
- have certain x-ray tests with injectable dyes or contrast agents.
- have surgery or other procedure for which you need to restrict the amount of food and liquid you eat and drink.
- have congestive heart failure.
- have a heart attack, severe infection, or stroke.
- are 65 years of age or older.

Tell your healthcare provider if you have any of the problems in the list above. Tell your healthcare provider that you are taking SYNJARDY or SYNJARDY XR before you have surgery or x-ray tests. Your healthcare provider may need to stop your SYNJARDY or SYNJARDY XR for a while if you have surgery or certain x-ray tests. SYNJARDY or SYNJARDY XR can have other serious side effects. See "What are the possible side effects of SYNJARDY or SYNJARDY XR?"

- Diabetic ketoacidosis (increased ketones in your blood or urine) in people with type 1 and other ketoacidosis. SYNJARDY or SYNJARDY XR can cause ketoacidosis that can be life-threatening and may lead to death. Ketoacidosis is a serious condition which needs to be treated in a hospital. People with type 1 diabetes have a high risk of getting ketoacidosis. People with type 2 diabetes or pancreas problems also have an increased risk of getting ketoacidosis. Ketoacidosis can also happen in people who: are sick, cannot eat or drink as usual, skip meals, are on a diet high in fat and low in carbohydrates (ketogenic diet), take less than the usual amount of insulin or miss insulin doses, drink too much alcohol, have a loss of too much fluid from the body (volume depletion), or who have surgery. Ketoacidosis can happen even if your blood sugar is less than 250 mg/dL. Your healthcare provider may ask you to periodically check ketones in your urine or blood.
  Stop taking SYNJARDY or SYNJARDY XR and call your healthcare provider or get medical help right away if you get any of the following. If possible, check for ketones in your urine or blood, even if your blood sugar is less than 250 mg/dL:

- nausea
- vomiting
- stomach-area (abdominal) pain

- tiredness
- trouble breathing
- ketones in your urine or blood

- Dehydration. SYNJARDY or SYNJARDY XR can cause some people to become dehydrated (the loss of body water and salt). Dehydration may cause you to feel dizzy, faint, light-headed, or weak, especially when you stand up (orthostatic hypotension). There have been reports of sudden worsening of kidney function in people who are taking SYNJARDY or SYNJARDY XR. You may be at higher risk of dehydration if you:
  - take medicines to lower your blood pressure, including diuretics (water pills)
  - are on a low sodium (salt) diet
  - have kidney problems
  - are 65 years of age or older
  Talk to your healthcare provider about what you can do to prevent dehydration including how much fluid you should drink on a daily basis. Call your healthcare provider right away if you reduce the amount of food or liquid you drink, for example if you are sick or you cannot eat, or start to lose liquids from your body, for example from vomiting, diarrhea or being in the sun too long.

What is SYNJARDY or SYNJARDY XR?

- SYNJARDY is a prescription medicine that contains 2 diabetes medicines, empagliflozin (JARDIANCE) and metformin HCl immediate-release.
- SYNJARDY XR is a prescription medicine that contains 2 diabetes medicines, empagliflozin (JARDIANCE) and metformin HCl extended-release.
- SYNJARDY can be used along with diet and exercise to improve blood sugar (glucose) in adults and children who are 10 years of age and older with type 2 diabetes.
- SYNJARDY XR can be used along with diet and exercise to improve blood sugar (glucose) in adults with type 2 diabetes.
- One of the medicines in SYNJARDY and SYNJARDY XR, empagliflozin (JARDIANCE), can also be used in adults with type 2 diabetes:
  - who have known cardiovascular disease to reduce the risk of cardiovascular death.
  - who have heart failure (when the heart cannot pump enough blood to the rest of your body) to reduce the risk of cardiovascular death and hospitalization for heart failure.
  - to reduce the risk of further worsening of kidney disease, end-stage kidney disease (ESKD), death due to cardiovascular disease, and hospitalization in adults with chronic kidney disease.
- SYNJARDY or SYNJARDY XR is not for use to lower blood sugar (glucose) in people with type 1 diabetes. It may increase their risk of diabetic ketoacidosis (increased ketones in blood or urine).
- SYNJARDY or SYNJARDY XR is only for use in people with type 2 diabetes, because it contains the prescription medicine metformin HCl.
- One of the medicines in SYNJARDY or SYNJARDY XR, empagliflozin (JARDIANCE), is not for people with polycystic kidney disease, or who are taking or have recently received certain types of immunosuppressive therapy to treat kidney disease. Empagliflozin (JARDIANCE) is not expected to work if you have these conditions.
- It is not known if SYNJARDY is safe and effective in children under 10 years of age.
- It is not known if SYNJARDY XR is safe and effective in children.

Who should not take SYNJARDY or SYNJARDY XR?
Do not take SYNJARDY or SYNJARDY XR if you:

- have severe kidney problems.
- have a condition called metabolic acidosis or diabetic ketoacidosis (increased ketones in the blood or urine).
- are allergic to empagliflozin (JARDIANCE), metformin HCl, or any of the ingredients in SYNJARDY or SYNJARDY XR.
  See the end of this Medication Guide for a complete list of ingredients in SYNJARDY and SYNJARDY XR. Symptoms of a serious allergic reaction to SYNJARDY and SYNJARDY XR may include:
  - rash
  - raised, red areas on your skin (hives)
  - swelling of your face, lips, mouth, and throat that may cause difficulty in breathing or swallowing
  If you have any of these symptoms, stop taking SYNJARDY or SYNJARDY XR and call your healthcare provider right away or go to the nearest hospital emergency room.

What should I tell my healthcare provider before taking SYNJARDY or SYNJARDY XR?
Before taking SYNJARDY or SYNJARDY XR, tell your healthcare provider about all of your medical conditions, including if you:

- have type 1 diabetes or have had diabetic ketoacidosis.
- have a decrease in your insulin dose.
- have a serious infection.
- have a history of infection of the vagina or penis.
- have a history of amputation.
- have kidney problems.
- have liver problems.
- have heart problems, including congestive heart failure.
- are 65 years of age or older.
- have a history of urinary tract infections or problems with urination.
- are on a low sodium (salt) diet. Your healthcare provider may change your diet or your dose.
- are going to have surgery. Your healthcare provider may stop your SYNJARDY or SYNJARDY XR before you have surgery. Talk to your healthcare provider if you are having surgery about when to stop taking SYNJARDY or SYNJARDY XR and when to start it again.
- are eating less, or there is a change in your diet.
- are dehydrated.
- have or have had problems with your pancreas, including pancreatitis or surgery on your pancreas.
- drink alcohol very often or drink a lot of alcohol in the short term ("binge" drinking).
- have ever had an allergic reaction to SYNJARDY or SYNJARDY XR.
- are going to get an injection of dye or contrast agents for an x-ray procedure. SYNJARDY or SYNJARDY XR may need to be stopped for a short time. Talk to your healthcare provider about when you should stop SYNJARDY or SYNJARDY XR and when you should start SYNJARDY or SYNJARDY XR again. See "What is the most important information I should know about SYNJARDY or SYNJARDY XR?"
- have low levels of vitamin B12 in your blood.
- are pregnant or plan to become pregnant. SYNJARDY or SYNJARDY XR may harm your unborn baby. If you become pregnant while taking SYNJARDY or SYNJARDY XR, tell your healthcare provider as soon as possible. Talk with your healthcare provider about the best way to control your blood sugar while you are pregnant.
- are breastfeeding or plan to breastfeed. SYNJARDY or SYNJARDY XR may pass into your breast milk and may harm your baby. Talk with your healthcare provider about the best way to feed your baby if you are taking SYNJARDY or SYNJARDY XR. Do not breastfeed while taking SYNJARDY or SYNJARDY XR.
- are a person who has not gone through menopause (premenopausal) who does not have periods regularly or at all. SYNJARDY or SYNJARDY XR can cause the release of an egg from an ovary in a person (ovulation). This can increase your chance of getting pregnant. Tell your healthcare provider right away if you become pregnant while taking SYNJARDY or SYNJARDY XR.

Tell your healthcare provider about all the medicines you take, including prescription and over-the-counter medicines, vitamins, and herbal supplements.
SYNJARDY or SYNJARDY XR may affect the way other medicines work, and other medicines may affect how SYNJARDY or SYNJARDY XR works. Know the medicines you take. Keep a list of them to show your healthcare provider and pharmacist when you get a new medicine.

How should I take SYNJARDY or SYNJARDY XR?

- Take SYNJARDY or SYNJARDY XR exactly as your healthcare provider tells you to take it.
- If you are prescribed SYNJARDY:
  - take SYNJARDY by mouth 2 times each day with meals. Taking SYNJARDY with meals may lower your chance of having an upset stomach.
- If you are prescribed SYNJARDY XR:
  - take SYNJARDY XR by mouth 1 time each day with a meal in the morning. Taking SYNJARDY XR with a meal may lower your chance of having an upset stomach.
  - swallow SYNJARDY XR tablets whole. Do not break, cut, crush, dissolve, or chew SYNJARDY XR tablets. If you cannot swallow SYNJARDY XR tablets whole, tell your healthcare provider.
  - you may see something that looks like the SYNJARDY XR tablet in your stool (bowel movement). This is not harmful and should not affect the way SYNJARDY XR works to control your diabetes.
- Your healthcare provider will tell you how much SYNJARDY or SYNJARDY XR to take and when to take it. Your healthcare provider may change your dose if needed.
- Your healthcare provider may tell you to take SYNJARDY or SYNJARDY XR along with other diabetes medicines. Low blood sugar can happen more often when SYNJARDY or SYNJARDY XR is taken with certain other diabetes medicines. See "What are the possible side effects of SYNJARDY or SYNJARDY XR?"
- If you miss a dose, take it as soon as you remember. If it is almost time for your next dose, skip the missed dose and take the medicine at the next regularly scheduled time. Do not take two doses of SYNJARDY or SYNJARDY XR at the same time. Talk with your healthcare provider if you have questions about a missed dose.
- If you take too much SYNJARDY or SYNJARDY XR, call your healthcare provider or Poison Help line at 1-800-222-1222, or go to the nearest hospital emergency room right away.
- When taking SYNJARDY or SYNJARDY XR, you may have sugar in your urine, which will show up on a urine test.
- When your body is under some types of stress, such as fever, trauma (such as a car accident), infection, or surgery, the amount of diabetes medicine you need may change. Tell your healthcare provider right away if you have any of these conditions and follow your healthcare provider's instructions.
- Your healthcare provider may do certain blood tests before you start SYNJARDY or SYNJARDY XR and during your treatment as needed.

What should I avoid while taking SYNJARDY or SYNJARDY XR?
Avoid drinking alcohol very often, or drinking a lot of alcohol in a short period of time ("binge" drinking). It can increase your chances of getting serious side effects.

What are the possible side effects of SYNJARDY or SYNJARDY XR?
SYNJARDY or SYNJARDY XR may cause serious side effects, including:

- See "What is the most important information I should know about SYNJARDY or SYNJARDY XR?"
- Genital and urinary tract infections. Empagliflozin, one of the medicines in SYNJARDY and SYNJARDY XR, can cause serious infections in your genital area or urinary tract that could require hospitalization. A rare but serious bacterial infection called necrotizing fasciitis can cause damage to the tissue under the skin in the area between and around the anus and genitals (perineum). This infection may require hospitalization, multiple surgeries, and could lead to death. Seek medical attention immediately if you have a fever or you are feeling very weak, tired or uncomfortable (malaise), and you develop any of the following symptoms in the area between and around your anus and genitals:

- pain or tenderness

- swelling

- redness of skin (erythema)

Also tell your healthcare provider if you have any of these signs or symptoms of urinary tract infections or yeast infections:

- Urinary tract infection:

- burning feeling when you urinate
- need to urinate often or right away
- pain in the lower part of your stomach (pelvis)
- blood in your urine

You may also have a fever, back pain, nausea, or vomiting.

- Vaginal yeast infection:

- vaginal odor
- white or yellowish vaginal discharge (may be lumpy or look like cottage cheese)
- vaginal itching

- Yeast infection of the skin around the penis (balanitis or balanoposthitis): If you are uncircumcised, swelling may make it difficult to pull back the skin around the tip of your penis. Other symptoms include:

- redness, itching, or swelling of the penis
- bad smelling discharge from the penis

- rash on the penis
- pain in the skin around the penis

Talk to your healthcare provider about what to do if you get symptoms of a yeast infection. They may suggest you use an over-the-counter antifungal medicine. Contact your healthcare provider right away if your symptoms do not improve after using an over-the-counter antifungal medicine.

- Low blood sugar (hypoglycemia). In adults, if you take SYNJARDY or SYNJARDY XR with another medicine that can cause low blood sugar, such as a sulfonylurea or insulin, your risk of getting low blood sugar is higher. In children 10 years of age and older, the risk for low blood sugar is higher with SYNJARDY even if you do not use another medicine that can also lower blood sugar. The dose of your sulfonylurea medicine or insulin may need to be lowered while you take SYNJARDY or SYNJARDY XR.
  Signs and symptoms of low blood sugar may include:

- headache
- drowsiness
- weakness

- irritability
- hunger
- fast heartbeat

- confusion
- shaking or feeling jittery

- dizziness
- sweating

- Amputations. SGLT2 inhibitors may increase your risk of lower limb amputations.
  You may be at a higher risk of lower limb amputation if you:
  - have a history of amputation
  - have had blocked or narrowed blood vessels, usually in your leg
  - have had diabetic foot infection, ulcers or sores
  Call your healthcare provider right away if you have new pain or tenderness, any sores, ulcers, or infections in your leg or foot. Talk to your healthcare provider about proper foot care.
- Serious allergic reactions. If you have any symptoms of a serious allergic reaction, stop taking SYNJARDY or SYNJARDY XR and call your healthcare provider right away or go to the nearest hospital emergency room. See "Who should not take SYNJARDY or SYNJARDY XR?".
- Low vitamin B12 (vitamin B12 deficiency). Using metformin for long periods of time may cause a decrease in the amount of vitamin B12 in your blood, especially if you have had low vitamin B12 blood levels before. Your healthcare provider may do blood tests to check your vitamin B12 levels.

The most common side effects of SYNJARDY or SYNJARDY XR include:

- low blood sugar
- urinary tract infections
- stuffy or runny nose and sore throat
- yeast infections in females
- diarrhea
- nausea or vomiting

- gas
- stomach discomfort
- indigestion
- weakness
- headache

These are not all the possible side effects of SYNJARDY or SYNJARDY XR. For more information, ask your healthcare provider or pharmacist.
Call your doctor for medical advice about side effects. You may report side effects to FDA at 1-800-FDA-1088.

How should I store SYNJARDY or SYNJARDY XR?

- Store SYNJARDY or SYNJARDY XR at room temperature between 68°F to 77°F (20°C to 25°C).
- Keep SYNJARDY or SYNJARDY XR and all medicines out of the reach of children.

General information about the safe and effective use of SYNJARDY or SYNJARDY XR.
Medicines are sometimes prescribed for purposes other than those listed in a Medication Guide. Do not use SYNJARDY or SYNJARDY XR for a condition for which it was not prescribed. Do not give SYNJARDY or SYNJARDY XR to other people, even if they have the same symptoms that you have. It may harm them.
You can ask your pharmacist or healthcare provider for information about SYNJARDY or SYNJARDY XR that is written for health professionals.

What are the ingredients in SYNJARDY?
Active Ingredients: empagliflozin and metformin HCl
Inactive Ingredients: colloidal silicon dioxide, copovidone, corn starch, and magnesium stearate. In addition, the film coating contains the following inactive ingredients: hypromellose, polyethylene glycol 400, talc, and titanium dioxide. 5 mg/500 mg and 5 mg/1,000 mg tablets also contain ferric oxide yellow. 12.5 mg/500 mg and 12.5 mg/1,000 mg tablets also contain black ferrosoferric oxide and ferric oxide red.
What are the ingredients in SYNJARDY XR?
Active Ingredients: empagliflozin and metformin HCl
Inactive Ingredients: Tablet core contains: hypromellose, magnesium stearate, and polyethylene oxide. The film coatings and printing ink contain: carnauba wax, FD&C blue#2/indigo carmine aluminum lake (12.5 mg/1,000 mg, 25 mg/1,000 mg), ferric oxide red (10 mg/1,000 mg), ferric oxide yellow (5 mg/1,000 mg, 10 mg/1,000 mg, 25 mg/1,000 mg), ferrosoferric oxide, hypromellose, isopropyl alcohol, polydextrose, polyethylene glycol, propylene glycol, purified water, talc, and titanium dioxide.

Distributed by: Boehringer Ingelheim Pharmaceuticals, Inc., Ridgefield, CT 06877 USA
Licensed from: Boehringer Ingelheim International GmbH, Ingelheim, Germany
SYNJARDY is a registered trademark of and used under license from Boehringer Ingelheim International GmbH.
Boehringer Ingelheim Pharmaceuticals, Inc. either owns or uses the Jardiance®, EMPA-REG OUTCOME®, EMPEROR-Reduced®, EMPEROR-Preserved®, and EMPA-KIDNEY® trademarks under license.
The other brands listed are trademarks of their respective owners and are not trademarks of Boehringer Ingelheim Pharmaceuticals, Inc.
Copyright © 2026 Boehringer Ingelheim International GmbH ALL RIGHTS RESERVED
COL12574FA072026
For more information about SYNJARDY or SYNJARDY XR, including current prescribing information and Medication Guide, go to www.synjardy.com or www.synjardyxr.com, scan the code, or call Boehringer Ingelheim Pharmaceuticals, Inc. at 1-800-542-6257.

This Medication Guide has been approved by the U.S. Food and Drug Administration.

Revised: January 2026

PRINCIPAL DISPLAY PANEL - 10 mg/1,000 mg Tablet Bottle Label

NDC 0597-0280-73

DISPENSE WITH ACCOMPANYING MEDICATION GUIDE

Synjardy®XR
(empagliflozin and metformin
hydrochloride extended-release tablets)

10 mg/1,000 mg*

Rx only

30 tablets

Boehringer
Ingelheim

PRINCIPAL DISPLAY PANEL - 5 mg/1,000 mg Tablet Bottle Label

NDC 0597-0290-74

DISPENSE WITH ACCOMPANYING
MEDICATION GUIDE

Synjardy®XR
(empagliflozin and metformin
hydrochloride extended-release
tablets)

5 mg/1,000 mg*

Rx only

60 tablets

Boehringer
Ingelheim

PRINCIPAL DISPLAY PANEL - 25 mg/1,000 mg Tablet Bottle Label

NDC 0597-0295-88

DISPENSE WITH ACCOMPANYING MEDICATION GUIDE

Synjardy®XR
(empagliflozin and metformin
hydrochloride extended-release tablets)

25 mg/1,000 mg*

Rx only

30 tablets

Boehringer
Ingelheim

PRINCIPAL DISPLAY PANEL - 12.5 mg/1,000 mg Tablet Bottle Label

NDC 0597-0300-45

DISPENSE WITH ACCOMPANYING
MEDICATION GUIDE

Synjardy®XR
(empagliflozin and metformin
hydrochloride extended-release
tablets)

12.5 mg/1,000 mg*

Rx only

60 tablets

Boehringer
Ingelheim